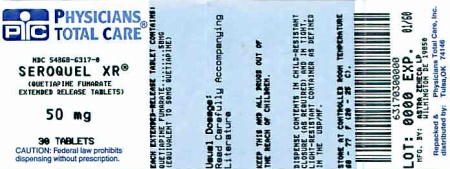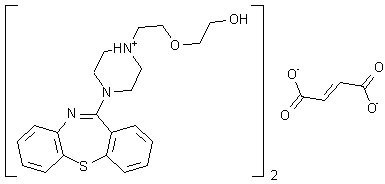 DRUG LABEL: SEROQUEL
NDC: 54868-6317 | Form: TABLET, EXTENDED RELEASE
Manufacturer: Physicians Total Care, Inc.
Category: prescription | Type: HUMAN PRESCRIPTION DRUG LABEL
Date: 20120206

ACTIVE INGREDIENTS: QUETIAPINE FUMARATE 50 mg/1 1
INACTIVE INGREDIENTS: LACTOSE MONOHYDRATE; CELLULOSE, MICROCRYSTALLINE; SODIUM CITRATE; HYPROMELLOSES; MAGNESIUM STEARATE; POLYETHYLENE GLYCOL 400; TITANIUM DIOXIDE; FERRIC OXIDE RED; FERRIC OXIDE YELLOW; WATER

HIGHLIGHTS OF PRESCRIBING INFORMATION

These highlights do not include all the information needed to use SEROQUEL XR safely and effectively. See full prescribing information for SEROQUEL XR.
SEROQUEL XR® (quetiapine fumarate) Extended-Release Tablets
Initial U.S. Approval: 1997

WARNING: INCREASED MORTALITY IN ELDERLY PATIENTS WITH DEMENTIA-RELATED PSYCHOSIS See full prescribing information for complete boxed warning.

- Antipsychotic drugs are associated with an increased risk of death. (5.1)
- Quetiapine is not approved for elderly patients with Dementia-Related Psychosis. (5.1)

WARNING: SUICIDALITY AND ANTIDEPRESSANT DRUGS See full prescribing information for complete boxed warning.

- Increased risk of suicidal thinking and behavior in children, adolescents and young adults taking antidepressants for major depressive disorder and other psychiatric disorders. (5.2)

Recent Major Changes

Warnings and Precautions, Hyperglycemia (5.4), 1/2011

Warnings and Precautions, Hyperlipidemia (5.5), 1/2011

Warnings and Precautions, Weight Gain (5.6), 1/2011

Warnings and Precautions, QT Prolongation (5.12), 7/2011

Warnings and Precautions, Hypothyroidism, (5.14), 1/2011

Warnings and Precautions, Withdrawal (5.23), 05/2010

1 INDICATIONS AND USAGE

SEROQUEL XR is an atypical antipsychotic indicated for the:

Treatment of schizophrenia (1.1)

• Adults: Efficacy was established with SEROQUEL XR in one 6-week and one maintenance trial in patients with schizophrenia as well as in three 6-week trials with SEROQUEL in patients with schizophrenia (14.1)

Acute treatment of manic or mixed episodes associated with bipolar I disorder, both as monotherapy and as an adjunct to lithium or divalproex (1.2)

• Adults: Efficacy was established with SEROQUEL XR in one 3-week trial in patients with manic or mixed episodes associated with bipolar I disorder as well as two 12-week monotherapy trials and one 3-week adjunctive trial with SEROQUEL in patients with manic episodes associated with bipolar I disorder (14.2)

Acute treatment of depressive episodes associated with bipolar disorder (1.2)

• Adults: Efficacy was established with SEROQUEL XR in one 8-week trial in patients with bipolar I or II disorder as well as two 8-week trials with SEROQUEL in patients with bipolar I or II disorder (14.2)

Maintenance treatment of bipolar I disorder as an adjunct to lithium or divalproex (1.2)

• Adults: Efficacy was established with SEROQUEL in two maintenance trials in patients with bipolar I disorder (14.2)

Adjunctive treatment of major depressive disorder (MDD) (1.3)

• Adults: Efficacy as an adjunct to antidepressants was established in two 6-week trials in patients with MDD who had an inadequate response to an antidepressant alone (14.3)

2 DOSAGE AND ADMINISTRATION

SEROQUEL XR Tablets should be swallowed whole and not split, chewed or crushed. SEROQUEL XR should be taken without food or with a light meal (approx. 300 calories). SEROQUEL XR should be administered once daily, preferably in the evening.

Indication | Dosing Instructions | Recommended Dose / Dose Range
Schizophrenia (2.1) | Day 1: 300 mg/day; Dose increases can be made at intervals as short as 1 day and in increments of up to 300 mg/day. | 400-800 mg/day
Schizophrenia Maintenance (Monotherapy) (2.1) | 400 mg/day to 800 mg/day | 400-800 mg/day
Bipolar Mania-; Acute monotherapy or as an adjunct to lithium or divalproex (2.2) | Day 1: 300 mg.; Day 2: 600 mg.; Day 3: between 400 mg and 800 mg | 400-800 mg/day
Depressive Episodes Associated with Bipolar Disorder (2.2) | Day 1: 50 mg; Day 2: 100 mg; Day 3: 200 mg; Day 4: 300 mg | 300 mg/day
Bipolar I Disorder-; Maintenance Treatment as an adjunct to lithium or divalproex (2.2) | 400 mg/day to 800 mg/day | 400-800 mg/day
Major Depressive Disorder, Adjunctive Therapy with Antidepressants (2.3) | Day 1 and 2: 50 mg; Day 3 and 4: 150 mg | 150-300 mg/day

3 DOSAGE FORMS AND STRENGTHS

Extended-Release Tablets: 50 mg, 150 mg, 200 mg, 300 mg, and 400 mg

4 CONTRAINDICATIONS

None (4)

5 WARNINGS AND PRECAUTIONS

- Increased Mortality in Elderly Patients with Dementia-Related Psychosis: Antipsychotic drugs, including quetiapine, are associated with an increased risk of death; causes of death are variable. (5.1)
- Suicidality and Antidepressant Drugs: Increased the risk of suicidal thinking and behavior in children, adolescents and young adults taking antidepressants for major depressive disorder and other psychiatric disorders. (5.2)
- Neuroleptic Malignant Syndrome (NMS): Manage with immediate discontinuation and close monitoring. (5.3)
- Hyperglycemia and Diabetes Mellitus (DM): Ketoacidosis, hyperosmolar coma and death have been reported in patients treated with atypical antipsychotics, including quetiapine. Any patient treated with atypical antipsychotics should be monitored for symptoms of hyperglycemia including polydipsia, polyuria, polyphagia, and weakness. When starting treatment, patients with diabetes or risk factors for diabetes should undergo blood glucose testing before and during treatment. (5.4)
- Hyperlipidemia: Undesirable alterations in lipids have been observed. Increases in total cholesterol, LDL-cholesterol and triglycerides and decreases in HDL-cholesterol have been reported in clinical trials. Appropriate clinical monitoring is recommended, including fasting blood lipid testing at the beginning of, and periodically, during treatment. (5.5)
- Weight Gain: Patients should receive regular monitoring of weight. (5.6)
- Tardive Dyskinesia: Discontinue if clinically appropriate. (5.7)
- Orthostatic Hypotension: Associated dizziness, tachycardia and syncope may occur especially during the initial dose titration period. Use in caution in patients with known cardiovascular or cerebrovascular disease. (5.8)
- Increased Blood Pressure in Children and Adolescents: Blood pressure should be measured at the beginning of, and periodically during treatment in children and adolescents. SEROQUEL XR has not been evaluated in pediatric patients. (5.9)
- Leukopenia, Neutropenia and Agranulocytosis: have been reported with atypical antipsychotics including SEROQUEL XR. Patients with a pre-existing low white cell count (WBC) or a history of leukopenia/neutropenia should have complete blood count (CBC) monitored frequently during the first few months of treatment and should discontinue SEROQUEL XR at the first sign of a decline in WBC in absence of other causative factors. (5.10)
- Cataracts: Lens changes have been observed in patients during long-term quetiapine treatment. Lens examination is recommended when starting treatment and at 6-month intervals during chronic treatment. (5.11)
- QT Prolongation: Post-marketing cases show increases in QT interval in patients who overdosed on quetiapine, in patients with concomitant illness, and in patients taking medicines known to cause electrolyte imbalance or increase QT interval. Avoid use with drugs that increase the QT interval and in patients with risk factors for prolonged QT interval. (5.12)
- Suicide: The possibility of a suicide attempt is inherent in schizophrenia, bipolar disorder and depression, and close supervision of high risk patients should accompany drug therapy. (5.21)
- See Full Prescribing Information for additional WARNINGS and PRECAUTIONS.

6 ADVERSE REACTIONS

Most common adverse reactions (incidence ≥5% and twice placebo) in decreasing frequency are: somnolence, dry mouth, constipation, dizziness, increased appetite, dyspepsia, weight gain, fatigue, dysarthria, and nasal congestion. (6.1)

To report SUSPECTED ADVERSE REACTIONS, contact AstraZeneca at 1-800-236-9933 or FDA at 1-800-FDA-1088 or www.fda.gov/medwatch.

7 DRUG INTERACTIONS

- P450 3A Inhibitors: May decrease the clearance of quetiapine. Lower doses of quetiapine may be required. (7.1)
- Hepatic Enzyme Inducers: May increase the clearance of quetiapine. Higher doses of quetiapine may be required with phenytoin or other inducers. (7.1)
- Centrally Acting Drugs: Caution should be used when quetiapine is used in combination with other CNS acting drugs. (7)
- Antihypertensive Agents: Quetiapine may add to the hypotensive effects of these agents. (7)
- Levodopa and Dopamine Agents: Quetiapine may antagonize the effect of these drugs. (7)
- Drugs known to cause electrolyte imbalance or increase QT interval: Caution should be used when quetiapine is used concomitantly with these drugs. (7)
- Interference with Urine Drug Screens: False positive urine drug screens using immunoassays for methadone or tricyclic antidepressants (TCAs) in patients taking quetiapine have been reported. (7)

8 USE IN SPECIFIC POPULATIONS

- Geriatric Use: Consider a lower starting dose (50 mg/day), slower titration, and careful monitoring during the initial dosing period in the elderly. (2.3 and 8.5)
- Hepatic Impairment: Lower starting dose (50 mg/day) and slower titration may be needed. (2.3, 8.7, 12.3)
- Pregnancy: Limited human data. Based on animal data, may cause fetal harm. Quetiapine should be used only if the potential benefit justifies the potential risk. (8.1)
- Nursing Mothers: Breastfeeding is not recommended. (8.3)
- Pediatric Use: Safety and effectiveness have not been established. (8.4)

FULL PRESCRIBING INFORMATION

WARNING: INCREASED MORTALITY IN ELDERLY PATIENTS WITH DEMENTIA-RELATED PSYCHOSIS

Elderly patients with dementia-related psychosis treated with antipsychotic drugs are at an increased risk of death. Analyses of seventeen placebo-controlled trials (modal duration of 10 weeks) largely in patients taking atypical antipsychotic drugs, revealed a risk of death in drug-treated patients of between 1.6 to 1.7 times the risk of death in placebo-treated patients. Over the course of a typical 10-week controlled trial, the rate of death in drug-treated patients was about 4.5%, compared to a rate of about 2.6% in the placebo group. Although the causes of death were varied, most of the deaths appeared to be either cardiovascular (e.g., heart failure, sudden death) or infectious (e.g., pneumonia) in nature. Observational studies suggest that, similar to atypical antipsychotic drugs, treatment with conventional antipsychotic drugs may increase mortality. The extent to which the findings of increased mortality in observational studies may be attributed to the antipsychotic drug as opposed to some characteristic(s) of the patients is not clear. SEROQUEL XR is not approved for the treatment of patients with dementia-related psychosis [see Warnings and Precautions (5.1)].

SUICIDALITY AND ANTIDEPRESSANT DRUGS

Antidepressants increased the risk compared to placebo of suicidal thinking and behavior (suicidality) in children, adolescents, and young adults in short-term studies of major depressive disorder (MDD) and other psychiatric disorders. Anyone considering the use of SEROQUEL XR or any other antidepressant in a child, adolescent, or young adult must balance this risk with the clinical need. Short-term studies did not show an increase in the risk of suicidality with antidepressants compared to placebo in adults beyond age 24; there was a reduction in risk with antidepressants compared to placebo in adults aged 65 and older. Depression and certain other psychiatric disorders are themselves associated with increases in the risk of suicide. Patients of all ages who are started on antidepressant therapy should be monitored appropriately and observed closely for clinical worsening, suicidality, or unusual changes in behavior. Families and caregivers should be advised of the need for close observation and communication with the prescriber. SEROQUEL XR is not approved for use in pediatric patients [see Warnings and Precautions (5.2)].

1 INDICATIONS AND USAGE

1.1 Schizophrenia

SEROQUEL XR is indicated for the treatment of schizophrenia. The efficacy of SEROQUEL XR in schizophrenia was established in one 6- week and one maintenance trial in adults with schizophrenia as well by extrapolation from three 6-week trials in adults with schizophrenia treated with SEROQUEL [see Clinical Studies (14.1)].

1.2 Bipolar Disorder

SEROQUEL XR is indicated for the acute treatment of manic or mixed episodes associated with bipolar I disorder, both as monotherapy and as an adjunct to lithium or divalproex. The efficacy of SEROQUEL XR in manic or mixed episodes of bipolar I disorder was established in one 3-week trial in adults with manic or mixed episodes associated with bipolar I disorder as well by extrapolation from two 12-week monotherapy and one 3-week adjunctive trial in adults with manic episodes associated with bipolar I disorder treated with SEROQUEL [see Clinical Studies (14.2)].

SEROQUEL XR is indicated for the acute treatment of depressive episodes associated with bipolar disorder. The efficacy of SEROQUEL XR was established in one 8-week trial in adults with bipolar I or II disorder as well as extrapolation from two 8-week trials in adults with bipolar I or II disorder treated with SEROQUEL [see Clinical Studies (14.2)].

SEROQUEL XR is indicated for the maintenance treatment of bipolar I disorder, as an adjunct to lithium or divalproex. Efficacy was extrapolated from two maintenance trials in adults with bipolar I disorder treated with SEROQUEL. The effectiveness of monotherapy for the maintenance treatment of bipolar disorder has not been systematically evaluated in controlled clinical trials [see Clinical Studies (14.2)].

1.3 Adjunctive Treatment of Major Depressive Disorder (MDD)

SEROQUEL XR is indicated for use as adjunctive therapy to antidepressants for the treatment of MDD. The efficacy of SEROQUEL XR as adjunctive therapy to antidepressants in MDD was established in two 6-week trials in adults with MDD who had an inadequate response to antidepressant treatment [see Clinical Studies (14.3)].

2 DOSAGE AND ADMINISTRATION

SEROQUEL XR tablets should be swallowed whole and not split, chewed or crushed.

It is recommended that SEROQUEL XR be taken without food or with a light meal (approximately 300 calories) [see Clinical Pharmacology (12.3)].

2.1 Schizophrenia

Dose Selection—SEROQUEL XR should be administered once daily, preferably in the evening. The recommended initial dose is 300 mg/day. Patients should be titrated within a dose range of 400 mg/day – 800 mg/day depending on the response and tolerance of the individual patient [see Clinical Studies (14.1)]. Dose increases can be made at intervals as short as 1 day and in increments of up to 300 mg/day. The safety of doses above 800 mg/day has not been evaluated in clinical trials.

Maintenance Treatment—A maintenance trial in adult patients with schizophrenia treated with SEROQUEL XR has shown this drug to be effective in delaying time to relapse in patients who were stabilized on SEROQUEL XR at doses of 400 mg/day to 800 mg/day for 16 weeks. Patients should be periodically reassessed to determine the need for maintenance treatment and the appropriate dose for such treatment [see Clinical Studies (14.1)].

2.2 Bipolar Disorder

Bipolar Mania

Usual Dose for Acute Monotherapy or Adjunct Therapy (with lithium or divalproex)

Dose Selection—When used as monotherapy or adjunct therapy (with lithium or divalproex), SEROQUEL XR should be administered once daily in the evening starting with 300 mg on Day 1 and 600 mg on Day 2. SEROQUEL XR can be adjusted between 400 mg and 800 mg beginning on Day 3 depending on the response and tolerance of the individual patient.

Recommended Dosing Schedule
Day | Day 1 | Day 2 | Day 3
SEROQUEL XR | 300 mg | 600 mg | 400 mg to 800 mg

Depressive Episodes Associated with Bipolar Disorder

Usual Dose—SEROQUEL XR should be administered once daily in the evening to reach 300 mg/day by Day 4.

Recommended Dosing Schedule
Day | Day 1 | Day 2 | Day 3 | Day 4
SEROQUEL XR | 50 mg | 100 mg | 200 mg | 300 mg

Maintenance Treatment for Bipolar I Disorder

Maintenance Treatment—Maintenance of efficacy in bipolar I disorder was demonstrated with SEROQUEL (administered twice daily totaling 400 mg/day to 800 mg/day) as adjunct therapy to lithium or divalproex. Generally, in the maintenance phase, patients continued on the same dose on which they were stabilized during the stabilization phase. Patients should be periodically reassessed to determine the need for maintenance treatment and the appropriate dose for such treatment [see Clinical Studies (14.2)].

2.3 Major Depressive Disorder, Adjunctive Therapy with Antidepressants

Dose Selection—SEROQUEL XR in a dose range of 150 mg/day to 300 mg/day was demonstrated to be effective as adjunctive therapy to antidepressants. Begin with 50 mg once daily in the evening. On Day 3, the dose can be increased to 150 mg once daily in the evening. There were dose-dependent increases in adverse reactions in the recommended dose range of 150 mg/day to 300 mg/day. Doses above 300 mg/day were not studied [see Clinical Studies (14.3)].

2.4 Dosing in Special Populations

Consideration should be given to a slower rate of dose titration and a lower target dose in the elderly and in patients who are debilitated or who have a predisposition to hypotensive reactions [see Use in Specific Populations (8.5, 8.7) and Clinical Pharmacology (12)]. When indicated, dose escalation should be performed with caution in these patients.

Elderly patients should be started on SEROQUEL XR 50 mg/day and the dose can be increased in increments of 50 mg/day depending on the response and tolerance of the individual patient.

Patients with hepatic impairment should be started on SEROQUEL XR 50 mg/day. The dose can be increased daily in increments of 50 mg/day to an effective dose, depending on the clinical response and tolerance of the patient.

The elimination of quetiapine was enhanced in the presence of phenytoin. Higher maintenance doses of quetiapine may be required when it is coadministered with phenytoin and other enzyme inducers such as carbamazepine and phenobarbital [see Drug Interactions (7.1)].

2.5 Re-initiation of Treatment in Patients Previously Discontinued

Although there are no data to specifically address reinitiation of treatment, it is recommended that when restarting therapy of patients who have been off SEROQUEL XR for more than one week, the initial dosing schedule should be followed. When restarting patients who have been off SEROQUEL XR for less than one week, gradual dose escalation may not be required and the maintenance dose may be reinitiated.

2.6 Switching Patients from SEROQUEL Tablets to SEROQUEL XR Tablets

Patients who are currently being treated with SEROQUEL (immediate release formulation) may be switched to SEROQUEL XR at the equivalent total daily dose taken once daily. Individual dosage adjustments may be necessary.

2.7 Switching from Antipsychotics

There are no systematically collected data to specifically address switching patients from other antipsychotics to SEROQUEL XR, or concerning concomitant administration with other antipsychotics. While immediate discontinuation of the previous antipsychotic treatment may be acceptable for some patients, more gradual discontinuation may be most appropriate for others. In all cases, the period of overlapping antipsychotic administration should be minimized. When switching patients from depot antipsychotics, if medically appropriate, initiate SEROQUEL XR therapy in place of the next scheduled injection. The need for continuing existing extrapyramidal syndrome medication should be re-evaluated periodically.

3 DOSAGE FORMS AND STRENGTHS

50 mg extended-release tablets

150 mg extended-release tablets

200 mg extended-release tablets

300 mg extended-release tablets

400 mg extended-release tablets

4 CONTRAINDICATIONS

None

5 WARNINGS AND PRECAUTIONS

5.1 Increased Mortality in Elderly Patients with Dementia-Related Psychosis

Elderly patients with dementia-related psychosis treated with antipsychotic drugs are at an increased risk of death compared to placebo. SEROQUEL XR (quetiapine fumarate) is not approved for the treatment of patients with dementia-related psychosis [see Boxed Warning].

5.2 Clinical Worsening and Suicide Risk

Patients with major depressive disorder (MDD), both adult and pediatric, may experience worsening of their depression and/or the emergence of suicidal ideation and behavior (suicidality) or unusual changes in behavior, whether or not they are taking antidepressant medications, and this risk may persist until significant remission occurs. Suicide is a known risk of depression and certain other psychiatric disorders, and these disorders themselves are the strongest predictors of suicide. There has been a long-standing concern, however, that antidepressants may have a role in inducing worsening of depression and the emergence of suicidality in certain patients during the early phases of treatment. Pooled analyses of short-term placebo-controlled trials of antidepressant drugs (SSRIs and others) showed that these drugs increase the risk of suicidal thinking and behavior (suicidality) in children, adolescents, and young adults (ages 18-24) with major depressive disorder (MDD) and other psychiatric disorders. Short-term studies did not show an increase in the risk of suicidality with antidepressants compared to placebo in adults beyond age 24; there was a reduction with antidepressants compared to placebo in adults aged 65 and older.

The pooled analyses of placebo-controlled trials in children and adolescents with MDD, obsessive compulsive disorder (OCD), or other psychiatric disorders included a total of 24 short-term trials of 9 antidepressant drugs in over 4400 patients. The pooled analyses of placebo-controlled trials in adults with MDD or other psychiatric disorders included a total of 295 short-term trials (median duration of 2 months) of 11 antidepressant drugs in over 77,000 patients. There was considerable variation in risk of suicidality among drugs, but a tendency toward an increase in the younger patients for almost all drugs studied. There were differences in absolute risk of suicidality across the different indications, with the highest incidence in MDD. The risk differences (drug vs. placebo), however, were relatively stable within age strata and across indications. These risk differences (drug-placebo difference in the number of cases of suicidality per 1000 patients treated) are provided in Table 1.

Table 1:
Age Range | Drug-Placebo Difference in Number of Cases of Suicidality per 1000 Patients Treated
 | Increases Compared to Placebo
<18 | 14 additional cases
18–24 | 5 additional cases
 | Decreases Compared to Placebo
25–64 | 1 fewer case
≥65 | 6 fewer cases

No suicides occurred in any of the pediatric trials. There were suicides in the adult trials, but the number was not sufficient to reach any conclusion about drug effect on suicide.

It is unknown whether the suicidality risk extends to longer-term use, i.e., beyond several months. However, there is substantial evidence from placebo-controlled maintenance trials in adults with depression that the use of antidepressants can delay the recurrence of depression.

All patients being treated with antidepressants for any indication should be monitored appropriately and observed closely for clinical worsening, suicidality, and unusual changes in behavior, especially during the initial few months of a course of drug therapy, or at times of dose changes, either increases or decreases.

The following symptoms, anxiety, agitation, panic attacks, insomnia, irritability, hostility, aggressiveness, impulsivity, akathisia (psychomotor restlessness), hypomania, and mania, have been reported in adult and pediatric patients being treated with antidepressants for major depressive disorder as well as for other indications, both psychiatric and nonpsychiatric. Although a causal link between the emergence of such symptoms and either the worsening of depression and/or the emergence of suicidal impulses has not been established, there is concern that such symptoms may represent precursors to emerging suicidality.

Consideration should be given to changing the therapeutic regimen, including possibly discontinuing the medication, in patients whose depression is persistently worse, or who are experiencing emergent suicidality or symptoms that might be precursors to worsening depression or suicidality, especially if these symptoms are severe, abrupt in onset, or were not part of the patient's presenting symptoms.

Families and caregivers of patients being treated with antidepressants for major depressive disorder or other indications, both psychiatric and nonpsychiatric, should be alerted about the need to monitor patients for the emergence of agitation, irritability, unusual changes in behavior, and the other symptoms described above, as well as the emergence of suicidality, and to report such symptoms immediately to healthcare providers. Such monitoring should include daily observation by families and caregivers. Prescriptions for SEROQUEL XR should be written for the smallest quantity of tablets consistent with good patient management, in order to reduce the risk of overdose.

Screening Patients for Bipolar Disorder: A major depressive episode may be the initial presentation of bipolar disorder. It is generally believed (though not established in controlled trials) that treating such an episode with an antidepressant alone may increase the likelihood of precipitation of a mixed/manic episode in patients at risk for bipolar disorder. Whether any of the symptoms described above represent such a conversion is unknown. However, prior to initiating treatment with an antidepressant, patients with depressive symptoms should be adequately screened to determine if they are at risk for bipolar disorder; such screening should include a detailed psychiatric history, including a family history of suicide, bipolar disorder, and depression.

5.3 Neuroleptic Malignant Syndrome (NMS)

A potentially fatal symptom complex sometimes referred to as Neuroleptic Malignant Syndrome (NMS) has been reported in association with administration of antipsychotic drugs, including quetiapine. Rare cases of NMS have been reported with quetiapine. Clinical manifestations of NMS are hyperpyrexia, muscle rigidity, altered mental status, and evidence of autonomic instability (irregular pulse or blood pressure, tachycardia, diaphoresis, and cardiac dysrhythmia). Additional signs may include elevated creatine phosphokinase, myoglobinuria (rhabdomyolysis) and acute renal failure.

The diagnostic evaluation of patients with this syndrome is complicated. In arriving at a diagnosis, it is important to exclude cases where the clinical presentation includes both serious medical illness (eg, pneumonia, systemic infection, etc.) and untreated or inadequately treated extrapyramidal signs and symptoms (EPS). Other important considerations in the differential diagnosis include central anticholinergic toxicity, heat stroke, drug fever and primary central nervous system (CNS) pathology.

The management of NMS should include: 1) immediate discontinuation of antipsychotic drugs and other drugs not essential to concurrent therapy; 2) intensive symptomatic treatment and medical monitoring; and 3) treatment of any concomitant serious medical problems for which specific treatments are available. There is no general agreement about specific pharmacological treatment regimens for NMS.

If a patient requires antipsychotic drug treatment after recovery from NMS, the potential reintroduction of drug therapy should be carefully considered. The patient should be carefully monitored since recurrences of NMS have been reported.

5.4 Hyperglycemia and Diabetes Mellitus

Hyperglycemia, in some cases extreme and associated with ketoacidosis or hyperosmolar coma or death, has been reported in patients treated with atypical antipsychotics, including quetiapine. Assessment of the relationship between atypical antipsychotic use and glucose abnormalities is complicated by the possibility of an increased background risk of diabetes mellitus in patients with schizophrenia and the increasing incidence of diabetes mellitus in the general population. Given these confounders, the relationship between atypical antipsychotic use and hyperglycemia-related adverse reactions is not completely understood. However, epidemiological studies suggest an increased risk of treatment-emergent hyperglycemia-related adverse reactions in patients treated with the atypical antipsychotics. Precise risk estimates for hyperglycemia-related adverse reactions in patients treated with atypical antipsychotics are not available.

Patients with an established diagnosis of diabetes mellitus who are started on atypical antipsychotics should be monitored regularly for worsening of glucose control. Patients with risk factors for diabetes mellitus (eg, obesity, family history of diabetes) who are starting treatment with atypical antipsychotics should undergo fasting blood glucose testing at the beginning of treatment and periodically during treatment. Any patient treated with atypical antipsychotics should be monitored for symptoms of hyperglycemia including polydipsia, polyuria, polyphagia, and weakness. Patients who develop symptoms of hyperglycemia during treatment with atypical antipsychotics should undergo fasting blood glucose testing. In some cases, hyperglycemia has resolved when the atypical antipsychotic was discontinued; however, some patients required continuation of anti-diabetic treatment despite discontinuation of the suspect drug.

In some patients, a worsening of more than one of the metabolic parameters of weight, blood glucose and lipids was observed in clinical studies. Changes in these parameters should be managed as clinically appropriate.

Adults:

Table 2: Fasting Glucose—Proportion of Patients Shifting to ≥ 126 mg/dL in short-term (≤ 12 weeks) Placebo-Controlled Studies

Laboratory Analyte | Category Change (At Least Once) from Baseline | Treatment Arm | N | Patients n (%)
Fasting Glucose | Normal to High; (<100 mg/dL to ≥ 126 mg/dL) | Quetiapine | 2907 | 71 (2.4%)
Fasting Glucose | Normal to High; (<100 mg/dL to ≥ 126 mg/dL) | Placebo | 1346 | 19 (1.4%)
Fasting Glucose | Borderline to High; (≥ 100 mg/dL and <126 mg/dL to ≥ 126 mg/dL) | Quetiapine | 572 | 67 (11.7%)
Fasting Glucose | Borderline to High; (≥ 100 mg/dL and <126 mg/dL to ≥ 126 mg/dL) | Placebo | 279 | 33 (11.8%)

In a 24-week trial (active-controlled, 115 patients treated with SEROQUEL) designed to evaluate glycemic status with oral glucose tolerance testing of all patients, at week 24 the incidence of a treatment-emergent post-glucose challenge glucose level ≥ 200 mg/dL was 1.7% and the incidence of a fasting treatment-emergent blood glucose level ≥ 126 mg/dL was 2.6%. The mean change in fasting glucose from baseline was 3.2 mg/dL and mean change in 2 hour glucose from baseline was -1.8 mg/dL for quetiapine.

In 2 long-term placebo-controlled randomized withdrawal clinical trials for bipolar maintenance, mean exposure of 213 days for SEROQUEL (646 patients) and 152 days for placebo (680 patients), the mean change in glucose from baseline was +5.0 mg/dL for quetiapine and –0.05 mg/dL for placebo. The exposure-adjusted rate of any increased blood glucose level (≥ 126 mg/dL) for patients more than 8 hours since a meal (however, some patients may not have been precluded from calorie intake from fluids during fasting period) was 18.0 per 100 patient years for SEROQUEL (10.7% of patients; n=556) and 9.5 for placebo per 100 patient years (4.6% of patients; n=581).

Table 3 shows the percentage of patients with shifts in blood glucose to ≥ 126 mg/dL from normal baseline in MDD adjunct therapy trials by dose.

Table 3: Percentage of Patients with Shifts from Normal Baseline in Blood Glucose to ≥ 126 mg/dL (assumed fasting) in MDD Adjunct Therapy Trials by Dose

Laboratory Analyte | Treatment Arm | N | Patients n (%)
Blood Glucose ≥ 126 mg/dL | Placebo | 277 | 17 (6%)
Blood Glucose ≥ 126 mg/dL | SEROQUEL XR 150 mg | 280 | 19 (7%)
Blood Glucose ≥ 126 mg/dL | SEROQUEL XR 300 mg | 269 | 32 (12%)

Children and Adolescents: Safety and effectiveness of SEROQUEL XR have not been established in pediatric patients and SEROQUEL XR is not approved for patients under the age of 18 years. In a placebo-controlled SEROQUEL monotherapy study of adolescent patients (13– 17 years of age) with schizophrenia (6 weeks duration), the mean change in fasting glucose levels for SEROQUEL (n=138) compared to placebo (n=67) was –0.75 mg/dL versus –1.70 mg/dL. In a placebo-controlled SEROQUEL monotherapy study of children and adolescent patients (10–17 years of age) with bipolar mania (3 weeks duration), the mean change in fasting glucose level for SEROQUEL (n=170) compared to placebo (n=81) was 3.62 mg/dL versus –1.17 mg/dL. No patient in either study with a baseline normal fasting glucose level (<100 mg/dL) or a baseline borderline fasting glucose level (≥100 mg/dL and <126 mg/dL) had a treatment-emergent blood glucose level of ≥126 mg/dL.

5.5 Hyperlipidemia

Undesirable alterations in lipids have been observed with quetiapine use. Clinical monitoring, including baseline and periodic follow-up lipid evaluations in patients using quetiapine is recommended.

In some patients, a worsening of more than one of the metabolic parameters of weight, blood glucose and lipids was observed in clinical studies. Changes in these parameters should be managed as clinically appropriate.

Adults:

Table 4 shows the percentage of patients with changes in cholesterol and triglycerides from baseline by indication in clinical trials with SEROQUEL XR.

Table 4: Percentage of Adult Patients with Shifts in Total Cholesterol, Triglycerides, LDL-Cholesterol and HDL-Cholesterol from Baseline to Clinically Significant Levels by Indication

Laboratory Analyte | Indication | Treatment Arm | N | Patients n (%)
Total Cholesterol ≥240 mg/dL | Schizophrenia [6 weeks duration] | SEROQUEL XR | 718 | 67 (9%)
Total Cholesterol ≥240 mg/dL | Schizophrenia [6 weeks duration] | Placebo | 232 | 21 (9%)
Total Cholesterol ≥240 mg/dL | Bipolar Depression [8 weeks duration] | SEROQUEL XR | 85 | 6 (7%)
Total Cholesterol ≥240 mg/dL | Bipolar Depression [8 weeks duration] | Placebo | 106 | 3 (3%)
Total Cholesterol ≥240 mg/dL | Bipolar Mania [3 weeks duration] | SEROQUEL XR | 128 | 9 (7%)
Total Cholesterol ≥240 mg/dL | Bipolar Mania [3 weeks duration] | Placebo | 134 | 5 (4%)
Total Cholesterol ≥240 mg/dL | Major Depressive Disorder (Adjunct Therapy) [6 weeks duration] | SEROQUEL XR | 420 | 67 (16%)
Total Cholesterol ≥240 mg/dL | Major Depressive Disorder (Adjunct Therapy) [6 weeks duration] | Placebo | 213 | 15 (7%)
Triglycerides ≥200 mg/dL | Schizophrenia | SEROQUEL XR | 659 | 118 (18%)
Triglycerides ≥200 mg/dL | Schizophrenia | Placebo | 214 | 11 (5%)
Triglycerides ≥200 mg/dL | Bipolar Depression | SEROQUEL XR | 84 | 7 (8%)
Triglycerides ≥200 mg/dL | Bipolar Depression | Placebo | 93 | 7 (8%)
Triglycerides ≥200 mg/dL | Bipolar Mania | SEROQUEL XR | 102 | 15 (15%)
Triglycerides ≥200 mg/dL | Bipolar Mania | Placebo | 125 | 8 (6%)
Triglycerides ≥200 mg/dL | Major Depressive Disorder (Adjunct Therapy) | SEROQUEL XR | 458 | 75 (16%)
Triglycerides ≥200 mg/dL | Major Depressive Disorder (Adjunct Therapy) | Placebo | 223 | 18 (8%)
LDL-Cholesterol ≥ 160 mg/dL | Schizophrenia | SEROQUEL XR | 691 | 47 (7%)
LDL-Cholesterol ≥ 160 mg/dL | Schizophrenia | Placebo | 227 | 17 (8%)
LDL-Cholesterol ≥ 160 mg/dL | Bipolar Depression | SEROQUEL XR | 86 | 3 (4%)
LDL-Cholesterol ≥ 160 mg/dL | Bipolar Depression | Placebo | 104 | 2 (2%)
LDL-Cholesterol ≥ 160 mg/dL | Bipolar Mania | SEROQUEL XR | 125 | 5 (4%)
LDL-Cholesterol ≥ 160 mg/dL | Bipolar Mania | Placebo | 135 | 2 (2%)
LDL-Cholesterol ≥ 160 mg/dL | Major Depressive Disorder (Adjunct Therapy) | SEROQUEL XR | 457 | 51 (11%)
LDL-Cholesterol ≥ 160 mg/dL | Major Depressive Disorder (Adjunct Therapy) | Placebo | 219 | 21 (10%)
HDL-Cholesterol ≤ 40 mg/dL | Schizophrenia | SEROQUEL XR | 600 | 87 (15%)
HDL-Cholesterol ≤ 40 mg/dL | Schizophrenia | Placebo | 195 | 23 (12%)
HDL-Cholesterol ≤ 40 mg/dL | Bipolar Depression | SEROQUEL XR | 78 | 7 (9%)
HDL-Cholesterol ≤ 40 mg/dL | Bipolar Depression | Placebo | 83 | 6 (7%)
HDL-Cholesterol ≤ 40 mg/dL | Bipolar Mania | SEROQUEL XR | 100 | 19 (19%)
HDL-Cholesterol ≤ 40 mg/dL | Bipolar Mania | Placebo | 115 | 15 (13%)
HDL-Cholesterol ≤ 40 mg/dL | Major Depressive Disorder (Adjunct Therapy) | SEROQUEL XR | 470 | 34 (7%)
HDL-Cholesterol ≤ 40 mg/dL | Major Depressive Disorder (Adjunct Therapy) | Placebo | 230 | 19 (8%)

In SEROQUEL clinical trials for schizophrenia, the percentage of patients with shifts in cholesterol and triglycerides from baseline to clinically significant levels were 18% (placebo: 7%) and 22% (placebo: 16%). HDL-cholesterol and LDL-cholesterol parameters were not measured in these studies. In SEROQUEL clinical trials for bipolar depression, the following percentage of patients had shifts from baseline to clinically significant levels for the four lipid parameters measured: total cholesterol 9% (placebo: 6%); triglycerides 14% (placebo: 9%); LDL-cholesterol 6% (placebo: 5%) and HDL-cholesterol 14% (placebo: 14%). Lipid parameters were not measured in the bipolar mania studies.

Table 5 shows the percentage of patients in MDD adjunctive therapy trials with clinically significant shifts in total-cholesterol, triglycerides, LDL-cholesterol and HDL-cholesterol from baseline by dose.

Table 5: Percentage of Patients with Shifts in Total Cholesterol, Triglycerides, LDL-Cholesterol and HDL-Cholesterol from Baseline to Clinically Significant Levels in MDD Adjunctive Therapy Trials by Dose

Laboratory Analyte | Treatment Arm | N | Patients n (%)
Cholesterol ≥ 240 mg/dL | Placebo | 213 | 15 (7%)
Cholesterol ≥ 240 mg/dL | SEROQUEL XR 150 mg | 223 | 41 (18%)
Cholesterol ≥ 240 mg/dL | SEROQUEL XR 300 mg | 197 | 26 (13%)
Triglycerides ≥ 200 mg/dL | Placebo | 223 | 18 (8%)
Triglycerides ≥ 200 mg/dL | SEROQUEL XR 150 mg | 232 | 36 (16%)
Triglycerides ≥ 200 mg/dL | SEROQUEL XR 300 mg | 226 | 39 (17%)
LDL-Cholesterol ≥ 160 mg/dL | Placebo | 219 | 21 (10%)
LDL-Cholesterol ≥ 160 mg/dL | SEROQUEL XR 150 mg | 242 | 29 (12%)
LDL-Cholesterol ≥ 160 mg/dL | SEROQUEL XR 300 mg | 215 | 22 (10%)
HDL-Cholesterol ≤ 40 mg/dL | Placebo | 230 | 19 (8%)
HDL-Cholesterol ≤ 40 mg/dL | SEROQUEL XR 150 mg | 238 | 14 (6%)
HDL-Cholesterol ≤ 40 mg/dL | SEROQUEL XR 300 mg | 232 | 20 (9%)

Children and Adolescents:

Safety and effectiveness of SEROQUEL XR have not been established in pediatric patients, and SEROQUEL XR is not approved for patients under the age of 18 years.

Table 6 shows the percentage of children and adolescents with shifts in total cholesterol, triglycerides, LDL-cholesterol and HDL-cholesterol from baseline to clinically significant levels by indication in clinical trials with SEROQUEL.

Table 6: Percentage of Children and Adolescents with Shifts in Total Cholesterol, Triglycerides LDL-Cholesterol and HDL-Cholesterol from Baseline to Clinically Significant Levels by Indication

Laboratory Analyte | Indication | Treatment Arm | N | Patients n (%)
Total Cholesterol ≥ 200 mg/dL | Schizophrenia [13- 17 years, 6 weeks duration] | SEROQUEL | 107 | 13 (12%)
Total Cholesterol ≥ 200 mg/dL | Schizophrenia [13- 17 years, 6 weeks duration] | Placebo | 56 | 1 (2%)
Total Cholesterol ≥ 200 mg/dL | Bipolar Mania [10-17 years, 3 weeks duration] | SEROQUEL | 159 | 16 (10%)
Total Cholesterol ≥ 200 mg/dL | Bipolar Mania [10-17 years, 3 weeks duration] | Placebo | 66 | 2 (3%)
Triglycerides ≥150 mg/dL | Schizophrenia | SEROQUEL | 103 | 17 (17%)
Triglycerides ≥150 mg/dL | Schizophrenia | Placebo | 51 | 4 (8%)
Triglycerides ≥150 mg/dL | Bipolar Mania | SEROQUEL | 149 | 32 (22%)
Triglycerides ≥150 mg/dL | Bipolar Mania | Placebo | 60 | 8 (13%)
LDL-Cholesterol ≥ 130 mg/dL | Schizophrenia | SEROQUEL | 112 | 4 (4%)
LDL-Cholesterol ≥ 130 mg/dL | Schizophrenia | Placebo | 60 | 1 (2%)
LDL-Cholesterol ≥ 130 mg/dL | Bipolar Mania | SEROQUEL | 169 | 13 (8%)
LDL-Cholesterol ≥ 130 mg/dL | Bipolar Mania | Placebo | 74 | 4 (5%)
HDL-Cholesterol ≤ 40 mg/dL | Schizophrenia | SEROQUEL | 104 | 16 (15%)
HDL-Cholesterol ≤ 40 mg/dL | Schizophrenia | Placebo | 54 | 10 (19%)
HDL-Cholesterol ≤ 40 mg/dL | Bipolar Mania | SEROQUEL | 154 | 16 (10%)
HDL-Cholesterol ≤ 40 mg/dL | Bipolar Mania | Placebo | 61 | 4 (7%)

5.6 Weight Gain

Increases in weight have been observed in clinical trials. Patients receiving quetiapine should receive regular monitoring of weight [see Patient Counseling Information (17)].

In some patients, a worsening of more than one of the metabolic parameters of weight, blood glucose and lipids was observed in clinical studies. Changes in these parameters should be managed as clinically appropriate.

Adults: Table 7 shows the percentage of adult patients with weight gain of ≥ 7% of body weight by indication.

Table 7: Percentage of Patients with Weight Gain ≥ 7% of Body Weight (Adults) by Indication

Vital sign | Indication | Treatment Arm | N | Patients n (%)
Weight Gain ≥ 7% of Body Weight | Schizophrenia | SEROQUEL XR | 907 | 90 (10%)
Weight Gain ≥ 7% of Body Weight | Schizophrenia | Placebo | 299 | 16 (5%)
Weight Gain ≥ 7% of Body Weight | Bipolar Mania | SEROQUEL XR | 138 | 7 (5%)
Weight Gain ≥ 7% of Body Weight | Bipolar Mania | Placebo | 150 | 0 (0%)
Weight Gain ≥ 7% of Body Weight | Bipolar Depression | SEROQUEL XR | 110 | 9 (8%)
Weight Gain ≥ 7% of Body Weight | Bipolar Depression | Placebo | 125 | 1 (1%)
Weight Gain ≥ 7% of Body Weight | Major Depressive Disorder (Adjunctive Therapy) | SEROQUEL XR | 616 | 32 (5%)
Weight Gain ≥ 7% of Body Weight | Major Depressive Disorder (Adjunctive Therapy) | Placebo | 302 | 5 (2%)

In schizophrenia trials, the proportions of patients meeting a weight gain criterion of ≥ 7% of body weight were compared in a pool of four 3- to 6-week placebo-controlled clinical trials, revealing a statistically significant greater incidence of weight gain for SEROQUEL (23%) compared to placebo (6%).

Table 8 shows the percentage of adult patients with weight gain of ≥ 7% of body weight for MDD by dose.

Table 8: Percentage of Patients with Weight Gain ≥ 7% of Body Weight in MDD Adjunctive Therapy Trials by Dose (Adults)

Vital sign | Treatment Arm | N | Patients n (%)
Weight Gain ≥7% of Body weight in MDD Adjunctive Therapy | Placebo | 302 | 5 (2%)
Weight Gain ≥7% of Body weight in MDD Adjunctive Therapy | SEROQUEL XR 150 mg | 309 | 10 (3%)
Weight Gain ≥7% of Body weight in MDD Adjunctive Therapy | SEROQUEL XR 300 mg | 307 | 22 (7%)

Children and Adolescents: Safety and effectiveness of SEROQUEL XR have not been established in pediatric patients and SEROQUEL XR is not approved for patients under the age of 18 years. In two clinical trials with SEROQUEL, one in bipolar mania and one in schizophrenia, reported increases in weight are included in table 9 below.

Table 9 shows the percentage of patients with weight gain ≥ 7% of body weight in clinical trials with SEROQUEL.

Table 9: Percentage of Patients with Weight Gain ≥ 7% of Body Weight (Children and Adolescents)

Vital Sign | Indication | Treatment Arm | N | Patients n (%)
Weight gain ≥ 7% of Body Weight | Schizophrenia | SEROQUEL | 111 | 23 (21%)
Weight gain ≥ 7% of Body Weight | Schizophrenia | Placebo | 44 | 3 (7%)
Weight gain ≥ 7% of Body Weight | Bipolar Mania | SEROQUEL | 157 | 18 (12%)
Weight gain ≥ 7% of Body Weight | Bipolar Mania | Placebo | 68 | 0 (0%)

The mean change in body weight in the schizophrenia trial was 2.0 kg in the SEROQUEL group and -0.4 kg in the placebo group and in the bipolar mania trial it was 1.7 kg in the SEROQUEL group and 0.4 kg in the placebo group.

In an open-label study that enrolled patients from the above two pediatric trials, 63% of patients (241/380) completed 26 weeks of therapy with SEROQUEL. After 26 weeks of treatment, the mean increase in body weight was 4.4 kg. Forty-five percent of the patients gained ≥ 7% of their body weight, not adjusted for normal growth. In order to adjust for normal growth over 26 weeks, an increase of at least 0.5 standard deviation from baseline in BMI was used as a measure of a clinically significant change; 18.3% of patients on SEROQUEL met this criterion after 26 weeks of treatment.

When treating pediatric patients with SEROQUEL for any indication, weight gain should be assessed against that expected for normal growth.

5.7 Tardive Dyskinesia

A syndrome of potentially irreversible, involuntary, dyskinetic movements may develop in patients treated with antipsychotic drugs including quetiapine. Although the prevalence of the syndrome appears to be highest among the elderly, especially elderly women, it is impossible to rely upon prevalence estimates to predict, at the inception of antipsychotic treatment, which patients are likely to develop the syndrome. Whether antipsychotic drug products differ in their potential to cause tardive dyskinesia is unknown.

The risk of developing tardive dyskinesia and the likelihood that it will become irreversible are believed to increase as the duration of treatment and the total cumulative dose of antipsychotic drugs administered to the patient increase. However, the syndrome can develop, although much less commonly, after relatively brief treatment periods at low doses or may even arise after discontinuation of treatment.

There is no known treatment for established cases of tardive dyskinesia, although the syndrome may remit, partially or completely, if antipsychotic treatment is withdrawn. Antipsychotic treatment, itself, however, may suppress (or partially suppress) the signs and symptoms of the syndrome and thereby may possibly mask the underlying process. The effect that symptomatic suppression has upon the long-term course of the syndrome is unknown.

Given these considerations, SEROQUEL XR should be prescribed in a manner that is most likely to minimize the occurrence of tardive dyskinesia. Chronic antipsychotic treatment should generally be reserved for patients who appear to suffer from a chronic illness that (1) is known to respond to antipsychotic drugs, and (2) for whom alternative, equally effective, but potentially less harmful treatments are not available or appropriate. In patients who do require chronic treatment, the smallest dose and the shortest duration of treatment producing a satisfactory clinical response should be sought. The need for continued treatment should be reassessed periodically.

If signs and symptoms of tardive dyskinesia appear in a patient on SEROQUEL XR, drug discontinuation should be considered. However, some patients may require treatment with quetiapine despite the presence of the syndrome.

5.8 Orthostatic Hypotension

Quetiapine may induce orthostatic hypotension associated with dizziness, tachycardia and, in some patients, syncope, especially during the initial dose-titration period, probably reflecting its ά1-adrenergic antagonist properties. Syncope was reported in 0.3% (5/1866) of the patients treated with SEROQUEL XR across all indications, compared with 0.2% (2/928) on placebo. Syncope was reported in 1% (28/3265) of the patients treated with SEROQUEL, compared with 0.2% (2/954) on placebo. Orthostatic hypotension, dizziness, and syncope may lead to falls.

Quetiapine should be used with particular caution in patients with known cardiovascular disease (history of myocardial infarction or ischemic heart disease, heart failure or conduction abnormalities), cerebrovascular disease or conditions which would predispose patients to hypotension (dehydration, hypovolemia and treatment with antihypertensive medications) [see Adverse Reactions (6.2)]. If hypotension occurs during titration to the target dose, a return to the previous dose in the titration schedule is appropriate.

5.9 Increases in Blood Pressure (Children and Adolescents)

Safety and effectiveness of SEROQUEL XR have not been established in pediatric patients and SEROQUEL XR is not approved for patients under the age of 18 years. In placebo-controlled trials in children and adolescents with schizophrenia (6-week duration) or bipolar mania (3- week duration), the incidence of increases at any time in systolic blood pressure (≥ 20 mmHg) was 15.2% (51/335) for SEROQUEL and 5.5% (9/163) for placebo; the incidence of increases at any time in diastolic blood pressure (≥ 10 mmHg) was 40.6% (136/335) for SEROQUEL and 24.5% (40/163) for placebo. In the 26-week open-label clinical trial, one child with a reported history of hypertension experienced a hypertensive crisis. Blood pressure in children and adolescents should be measured at the beginning of, and periodically during treatment.

5.10 Leukopenia, Neutropenia and Agranulocytosis

In clinical trials and postmarketing experience, events of leukopenia/neutropenia have been reported temporally related to atypical antipsychotic agents, including quetiapine fumarate. Agranulocytosis (including fatal cases) has also been reported.

Possible risk factors for leukopenia/neutropenia include pre-existing low white cell count (WBC) and history of drug induced leukopenia/neutropenia. Patients with a pre-existing low WBC or a history of drug induced leukopenia/neutropenia should have their complete blood count (CBC) monitored frequently during the first few months of therapy and should discontinue SEROQUEL XR at the first sign of a decline in WBC in absence of other causative factors.

Patients with neutropenia should be carefully monitored for fever or other symptoms or signs of infection and treated promptly if such symptoms or signs occur. Patients with severe neutropenia (absolute neutrophil count <1000/mm^3) should discontinue SEROQUEL XR and have their WBC followed until recovery [see Adverse Reactions (6.2)].

5.11 Cataracts

The development of cataracts was observed in association with quetiapine treatment in chronic dog studies [see Animal Toxicology (13.2)]. Lens changes have also been observed in adults, children, and adolescents during long-term quetiapine treatment, but a causal relationship to quetiapine use has not been established. Nevertheless, the possibility of lenticular changes cannot be excluded at this time. Therefore, examination of the lens by methods adequate to detect cataract formation, such as slit lamp exam or other appropriately sensitive methods, is recommended at initiation of treatment or shortly thereafter, and at 6-month intervals during chronic treatment.

5.12 QT Prolongation

In clinical trials quetiapine was not associated with a persistent increase in QT intervals. However, the QT effect was not systematically evaluated in a thorough QT study. In post marketing experience there were cases reported of QT prolongation in patients who overdosed on quetiapine [see Overdosage (10.1)], in patients with concomitant illness, and in patients taking medicines known to cause electrolyte imbalance or increase QT interval [see Drug Interactions (7)].

The use of quetiapine should be avoided in combination with other drugs that are known to prolong QTc including Class 1A antiarrythmics (e.g., quinidine, procainamide) or Class III antiarrythmics (e.g., amiodarone, sotalol), antipsychotic medications (e.g., ziprasidone, chlorpromazine, thioridazine), antibiotics (e.g., gatifloxacin, moxifloxacin), or any other class of medications known to prolong the QTc interval (e.g., pentamidine, levomethadyl acetate, methadone).

Quetiapine should also be avoided in circumstances that may increase the risk of occurrence of torsade de pointes and/or sudden death including (1) a history of cardiac arrhythmias such as bradycardia; (2) hypokalemia or hypomagnesemia; (3) concomitant use of other drugs that prolong the QTc interval; and (4) presence of congenital prolongation of the QT interval.

Caution should also be exercised when quetiapine is prescribed in patients with increased risk of QT prolongation (e.g. cardiovascular disease, family history of QT prolongation, the elderly, congestive heart failure and heart hypertrophy).

5.13 Seizures

During short-term clinical trials with SEROQUEL XR, seizures occurred in 0.05% (1/1866) of patients treated with SEROQUEL XR across all indications compared to 0.3% (3/928) on placebo. During clinical trials with SEROQUEL, seizures occurred in 0.5% (20/3490) of patients treated with SEROQUEL compared to 0.2% (2/954) on placebo. As with other antipsychotics, quetiapine fumarate should be used cautiously in patients with a history of seizures or with conditions that potentially lower the seizure threshold, e.g., Alzheimer’s dementia. Conditions that lower the seizure threshold may be more prevalent in a population of 65 years or older.

5.14 Hypothyroidism

Adults: Clinical trials with quetiapine demonstrated dose-related decreases in thyroid hormone levels. The reduction in total and free thyroxine (T4) of approximately 20% at the higher end of the therapeutic dose range was maximal in the first six weeks of treatment and maintained without adaptation or progression during more chronic therapy. In nearly all cases, cessation of quetiapine treatment was associated with a reversal of the effects on total and free T4, irrespective of the duration of treatment. In SEROQUEL XR clinical trials across all indications 1.8% (24/1336) of patients on SEROQUEL XR vs. 0.6% (3/530) on placebo experienced decreased free thyroxine and 1.6% (21/1346) on SEROQUEL XR vs. 3.4% (18/534) on placebo experienced increased thyroid stimulating hormone (TSH); however, no patients experienced a combination of clinically significant decreased free thyroxine and increased TSH. About 0.7% (26/3489) of SEROQUEL patients did experience TSH increases in monotherapy studies. Some patients with TSH increases needed replacement thyroid treatment.

In all quetiapine trials, the incidence of potentially clinically significant shifts in thyroid hormones and TSH were*: decrease in free T4, 2.0% (357/17513); decrease in total T4, 4.0% (75/1861); decrease in free T3, 0.4% (53/13766); decrease in total T3, 2.0% (26/1312), and increase in TSH, 4.9% (956/19412). In eight patients, where TBG was measured, levels of TBG were unchanged.

Table 10 shows the incidence of these shifts in short-term placebo-controlled clinical trials.

Table 10: Incidence of potentially clinically significant shifts in thyroid hormone levels and TSH in short term placebo-controlled clinical trials
Total T4 |  | Free T4 |  | Total T3 |  | Free T3 |  | TSH
Quetiapine | Placebo | Quetiapine | Placebo | Quetiapine | Placebo | Quetiapine | Placebo | Quetiapine | Placebo
3.4 %; (37/1097) | 0.6%; (4/651) | 0.7%; (52/7218) | 0.1%; (4/3668) | 0.5%; (2/369) | 0.0%; (0/113) | 0.2%; (11/5673) | 0.0%; (1/2679) | 3.2%; (240/7587) | 2.7%; (105/3912)

In short-term placebo-controlled monotherapy trials, the incidence of reciprocal, potentially clinically significant shifts in T3 and TSH was 0.0 % for both quetiapine (1/4800) and placebo (0/2190) and for T4 and TSH the shifts were 0.1% (7/6154) for quetiapine versus 0.0 % (1/3007) for placebo.

Generally, these changes in thyroid hormone levels were of no clinical significance.

Children and Adolescents: Safety and effectiveness of SEROQUEL XR have not been established in pediatric patients and SEROQUEL XR is not approved for patients under the age of 18 years. In acute placebo-controlled trials in children and adolescent patients with schizophrenia (6-week duration) or bipolar mania (3-week duration), the incidence of shifts to potentially clinically important thyroid function values at any time for SEROQUEL treated patients and placebo-treated patients for elevated TSH was 2.9% (8/280) vs. 0.7% (1/138), respectively and for decreased total thyroxine was 2.8% (8/289) vs. 0% (0/145), respectively. Of the SEROQUEL treated patients with elevated TSH levels, 1 had simultaneous low free T4 level at end of treatment.

5.15 Hyperprolactinemia

Adults: During clinical trials with quetiapine across all indications, the incidence of shifts in prolactin levels to a clinically significant value occurred in 3.6% (158/4416) of patients treated with quetiapine compared to 2.6% (51/1968) on placebo.

Children and Adolescents: Safety and effectiveness of SEROQUEL XR have not been established in pediatric patients and SEROQUEL XR is not approved for patients under the age of 18 years. In acute placebo-controlled trials in children and adolescent patients with bipolar mania (3-week duration) or schizophrenia (6-week duration), the incidence of shifts in prolactin levels to a clinically significant value (>20 μg/L males; > 26 μg/L females at any time) was 13.4% (18/134) for SEROQUEL compared to 4% (3/75) for placebo in males and 8.7% (9/104) for SEROQUEL compared to 0% (0/39) for placebo in females.

Like other drugs that antagonize dopamine D2 receptors, SEROQUEL XR elevates prolactin levels in some patients and the elevation may persist during chronic administration. Hyperprolactinemia, regardless of etiology, may suppress hypothalamic GnRH, resulting in reduced pituitary gonadotrophin secretion. This, in turn, may inhibit reproductive function by impairing gonadal steroidogenesis in both female and male patients. Galactorrhea, amenorrhea, gynecomastia, and impotence have been reported in patients receiving prolactin-elevating compounds. Long-standing hyperprolactinemia when associated with hypogonadism may lead to decreased bone density in both female and male subjects.

Tissue culture experiments indicate that approximately one-third of human breast cancers are prolactin dependent in vitro, a factor of potential importance if the prescription of these drugs is considered in a patient with previously detected breast cancer. As is common with compounds which increase prolactin release, mammary gland, and pancreatic islet cell neoplasia (mammary adenocarcinomas, pituitary and pancreatic adenomas) was observed in carcinogenicity studies conducted in mice and rats. Neither clinical studies nor epidemiologic studies conducted to date have shown an association between chronic administration of this class of drugs and tumorigenesis in humans, but the available evidence is too limited to be conclusive [see Carcinogenesis, Mutagenesis, Impairment of Fertility (13.1)].

5.16 Transaminase Elevations

Asymptomatic, transient and reversible elevations in serum transaminases (primarily ALT) have been reported. The proportions of patients with transaminase elevations of >3 times the upper limits of the normal reference range in a pool of placebo-controlled trials ranged between 1% and 2% for SEROQUEL XR compared to 2% for placebo. In schizophrenia trials in adults, the proportions of patients with transaminase elevations of >3 times the upper limits of the normal reference range in a pool of 3- to 6-week placebo-controlled trials were approximately 6% (29/483) for SEROQUEL compared to 1% (3/194) for placebo. These hepatic enzyme elevations usually occurred within the first 3 weeks of drug treatment and promptly returned to pre-study levels with ongoing treatment with quetiapine.

5.17 Potential for Cognitive and Motor Impairment

Somnolence was a commonly reported adverse event reported in patients treated with quetiapine especially during the 3-day period of initial dose titration. In schizophrenia trials, somnolence was reported in 24.7% (235/951) of patients on SEROQUEL XR compared to 10.3% (33/319) of placebo patients. In a bipolar depression clinical trial, somnolence was reported in 51.8% (71/137) of patients on SEROQUEL XR compared to 12.9% (18/140) of placebo patients. In a clinical trial for bipolar mania, somnolence was reported in 50.3% (76/151) of patients on SEROQUEL XR compared to 11.9% (19/160) of placebo patients. Since quetiapine has the potential to impair judgment, thinking, or motor skills, patients should be cautioned about performing activities requiring mental alertness, such as operating a motor vehicle (including automobiles) or operating hazardous machinery until they are reasonably certain that quetiapine therapy does not affect them adversely. Somnolence may lead to falls.

In short-term adjunctive therapy trials for MDD, somnolence was reported in 40% (252/627) of patients on SEROQUEL XR respectively compared to 9% (27/309) of placebo patients. Somnolence was dose-related in these trials (37% (117/315) and 43% (135/312) for the 150 mg and 300 mg groups, respectively).

5.18 Priapism

One case of priapism in a patient receiving quetiapine was reported prior to market introduction. While a causal relationship to use of quetiapine has not been established, other drugs with α-adrenergic blocking effects have been reported to induce priapism, and it is possible that quetiapine may share this capacity. Severe priapism may require surgical intervention.

5.19 Body Temperature Regulation

Disruption of the body's ability to reduce core body temperature has been attributed to antipsychotic agents. Appropriate care is advised when prescribing SEROQUEL XR for patients who will be experiencing conditions which may contribute to an elevation in core body temperature, eg, exercising strenuously, exposure to extreme heat, receiving concomitant medication with anticholinergic activity, or being subject to dehydration.

5.20 Dysphagia

Esophageal dysmotility and aspiration have been associated with antipsychotic drug use. Aspiration pneumonia is a common cause of morbidity and mortality in elderly patients, in particular those with advanced Alzheimer's dementia. SEROQUEL XR and other antipsychotic drugs should be used cautiously in patients at risk for aspiration pneumonia.

5.21 Suicide

The possibility of a suicide attempt is inherent in schizophrenia, bipolar disorder and depression; close supervision of high risk patients should accompany drug therapy. Prescriptions for SEROQUEL XR should be written for the smallest quantity of tablets consistent with good patient management in order to reduce the risk of overdose.

In three, 6-week clinical studies in patients with schizophrenia (N=951) the incidence of treatment emergent suicidal ideation or suicide attempt was 0.6% (n=6) in SEROQUEL XR treated patients and 0.9% (n=3) in placebo-treated patients.

In an 8-week clinical study in patients with bipolar depression (N=137 for SEROQUEL XR and 140 for placebo) the incidence of treatment emergent suicidal ideation or suicide attempt was 0.7% (n=1) for SEROQUEL XR treated patients and 1.4% (n=2) for placebo.

In a 3-week clinical study in patients with bipolar mania (N=311, 151 for SEROQUEL XR and 160 for placebo) the incidence of treatment emergent suicidal ideation or suicide attempt was 1.3% (n=2) for SEROQUEL XR compared to 3.8% (n=6) for placebo.

In two, 6-week MDD adjunctive therapy trials (n=936, 627 on SEROQUEL XR and 309 on placebo) the incidence of treatment emergent suicidal ideation or suicide attempt was 0.5% (n=3) in SEROQUEL XR treated patients and 0.6% (n=2) in placebo.

5.22 Use in Patients with Concomitant Illness

Clinical experience with SEROQUEL XR in patients with certain concomitant systemic illnesses [see Pharmacokinetics (12.3)] is limited.

SEROQUEL XR has not been evaluated or used to any appreciable extent in patients with a recent history of myocardial infarction or unstable heart disease. Patients with these diagnoses were excluded from premarketing clinical studies. Because of the risk of orthostatic hypotension with SEROQUEL XR, caution should be observed in cardiac patients [see Warnings and Precautions (5.8)].

5.23 Withdrawal

Acute withdrawal symptoms, such as insomnia, nausea and vomiting have been described after abrupt cessation of atypical antipsychotic drugs, including quetiapine fumarate. In short-term placebo-controlled, monotherapy clinical trials with SEROQUEL XR that included a discontinuation phase which evaluated discontinuation symptoms, the aggregated incidence of patients experiencing one or more discontinuation symptoms after abrupt cessation was 12.1% (241/1993) for SEROQUEL XR and 6.7% (71/1065) for placebo. The incidence of the individual adverse events (i.e., insomnia, nausea, headache, diarrhea, vomiting, dizziness and irritability) did not exceed 5.3% in any treatment group and usually resolved after 1 week post-discontinuation. Gradual withdrawal is advised.

6 ADVERSE REACTIONS

6.1 Clinical Studies Experience

Because clinical studies are conducted under widely varying conditions, adverse reaction rates observed in the clinical studies of a drug cannot be directly compared to rates in the clinical studies of another drug and may not reflect the rates observed in practice.

The information below is derived from a clinical trial database for SEROQUEL XR consisting of approximately 3400 patients exposed to SEROQUEL XR for the treatment of Schizophrenia, Bipolar Disorder, and Major Depressive Disorder in placebo-controlled trials. This experience corresponds to approximately 1020.1 patient-years. Adverse reactions were assessed by collecting adverse reactions, results of physical examinations, vital signs, body weights, laboratory analyses and ECG results.

Adverse reactions during exposure were obtained by general inquiry and recorded by clinical investigators using terminology of their own choosing. Consequently, it is not possible to provide a meaningful estimate of the proportion of individuals experiencing adverse reactions without first grouping similar types of reactions into a smaller number of standardized event categories. In the tables and tabulations that follow, standard MedDRA terminology has been used to classify reported adverse reactions.

The stated frequencies of adverse reactions represent the proportion of individuals who experienced, at least once, a treatment-emergent adverse reaction of the type listed. An event was considered treatment-emergent if it occurred for the first time or worsened while receiving therapy following baseline evaluation.

Adverse Reactions Associated with Discontinuation of Treatment in Short-Term, Placebo-Controlled Trials

Schizophrenia: There was no difference in the incidence and type of adverse reactions associated with discontinuation (6.4% (61/951) for SEROQUEL XR vs. 7.5% (24/319) for placebo) in a pool of controlled Schizophrenia trials. There were no adverse reactions leading to discontinuation that occurred at an incidence of ≥ 2% for SEROQUEL XR in Schizophrenia trials.

Bipolar Disorder:

Mania: In a single clinical trial in patients with bipolar mania, 4.6% (7/151) of patients on SEROQUEL XR discontinued due to an adverse reaction compared to 8.1% (13/160) on placebo. There were no adverse reactions leading to discontinuation that occurred at an incidence of ≥ 2% for SEROQUEL XR in the Bipolar Mania trial.

Depression: In a single clinical trial in patients with bipolar depression, 14% (19/137) of patients on SEROQUEL XR discontinued due to an adverse reaction compared to 4% (5/140) on placebo. Somnolence∗ was the only adverse reaction leading to discontinuation that occurred at an incidence of ≥ 2% in SEROQUEL XR in the Bipolar Depression trial.

∗ The adverse reaction term “somnolence” includes both “somnolence” and “sedation.”

MDD, Adjunctive Therapy: In adjunctive therapy clinical trials in patients with MDD, 12.1% (76/627) of patients on SEROQUEL XR discontinued due to adverse reaction compared to 1.9% (6/309) on placebo. Somnolence* was the only adverse reaction leading to discontinuation that occurred at an incidence of ≥ 2% in SEROQUEL XR in MDD trials.

Commonly Observed Adverse Reactions in Short-Term, Placebo-Controlled Trials:

In short-term placebo-controlled studies for schizophrenia the most commonly observed adverse reactions associated with the use of SEROQUEL XR (incidence of 5% or greater) and observed at a rate on SEROQUEL XR at least twice that of placebo were somnolence (25%), dry mouth (12%), dizziness (10%), and dyspepsia (5%).

Adverse Reactions Occurring at an Incidence of 1% or More Among SEROQUEL XR Treated Patients in Short-Term, Placebo-Controlled Trials

Table 11 enumerates the incidence, rounded to the nearest percent, of treatment-emergent adverse reactions that occurred during acute therapy of schizophrenia (up to 6 weeks) in 1% or more in patients treated with SEROQUEL XR (doses ranging from 300 to 800 mg/day) where the incidence in patients treated with SEROQUEL XR was greater than the incidence in placebo-treated patients.

Table 11: Treatment-Emergent Adverse Reaction Incidence in 6-Week Placebo-Controlled Clinical Trials for the Treatment of Schizophrenia
Body System/Preferred Term | Placebo | SEROQUEL XR
 | (n=319) | (n=951)
Cardiac Disorders
Tachycardia | 1% | 3%
Eye Disorders
Vision blurred | 1% | 2%
Gastrointestinal Disorders
Dry Mouth | 1% | 12%
Constipation | 5% | 6%
Dyspepsia | 2% | 5%
Toothache | 0% | 2%
General Disorders and Administration Site Conditions
Fatigue | 2% | 3%
Irritability | 0% | 1%
Pyrexia | 0% | 1%
Investigations
Heart Rate Increased | 1% | 4%
Metabolism and Nutrition Disorders
Increased Appetite | 0% | 2%
Musculoskeletal and Connective Tissue Disorders
Muscle Spasms | 1% | 2%
Nervous System Disorders
Somnolence | 10% | 25%
Dizziness | 4% | 10%
Tremor | 1% | 2%
Akathisia | 1% | 2%
Extrapyramidal Symptoms | 5% | 8%
Psychiatric Disorders
Anxiety | 1% | 2%
Schizophrenia | 1% | 2%
Restlessness | 1% | 2%
Vascular Disorders
Orthostatic Hypotension | 5% | 7%
Hypotension | 1% | 3%

In a 3-week, placebo-controlled study in bipolar mania the most commonly observed adverse reactions associated with the use of SEROQUEL XR (incidence of 5% or greater) and observed at a rate on SEROQUEL XR at least twice that of placebo were somnolence (50%), dry mouth (34%), dizziness (10%), constipation (10%), weight gain (7%), dysarthria (5%), and nasal congestion (5%).

Table 12 enumerates the incidence, rounded to the nearest percent, of treatment-emergent adverse reactions that occurred during acute therapy of bipolar mania (up to 3 weeks) in 1% or more of patients treated with SEROQUEL XR (doses ranging from 400 to 800 mg/day) where the incidence in patients treated with SEROQUEL XR was greater than the incidence in placebo-treated patients.

Table 12: Treatment-Emergent Adverse Reactions in a 3-Week Placebo-Controlled Clinical Trial for the Treatment of Bipolar Mania
Body System/Preferred Term | PLACEBO | SEROQUEL XR
 | (n=160) | (n=151)
Cardiac Disorders
Tachycardia | 1% | 2%
Eye Disorders
Vision blurred | 1% | 2%
Gastrointestinal Disorders
Dry Mouth | 7% | 34%
Constipation | 3% | 10%
Dyspepsia | 4% | 7%
Toothache | 1% | 3%
General Disorders and Administration Site Conditions
Fatigue | 4% | 7%
Sluggishness | 1% | 2%
Pain | 0% | 1%
Investigations
Weight Gain | 1% | 7%
Heart Rate Increased | 0% | 3%
Injury, Poisoning And Procedural Complications
Contusion | 0% | 1%
Metabolism And Nutrition Disorders
Increased Appetite | 2% | 4%
Nervous System Disorders
Extrapyramidal Symptoms | 4% | 7%
Somnolence | 12% | 50%
Dizziness | 4% | 10%
Dysarthria | 0% | 5%
Lethargy | 1% | 2%
Postural Dizziness | 0% | 1%
Musculoskeletal And Connective Tissue Disorders
Back Pain | 2% | 3%
Arthralgia | 0% | 1%
Psychiatric Disorders
Abnormal Dreams | 0% | 3%
Bipolar I Disorder | 0% | 1%
Respiratory, Thoracic and Mediastinal Disorders
Nasal Congestion | 1% | 5%
Dry Throat | 0% | 1%
Vascular Disorders
Orthostatic Hypotension | 0% | 3%

In the 8-week placebo-controlled bipolar depression study, the most commonly observed adverse reactions associated with the use of SEROQUEL XR (incidence of 5% or greater) and observed at a rate on SEROQUEL XR at least twice that of placebo were somnolence (52%), dry mouth (37%), increased appetite (12%), weight gain (7%), dyspepsia (7%), and fatigue (6%).

Table 13: enumerates the incidence, rounded to the nearest percent, of treatment-emergent adverse reactions that occurred during acute therapy of bipolar depression (up to 8 weeks) in 1% or more of patients treated with SEROQUEL XR 300 mg/day where the incidence in patients treated with SEROQUEL XR was greater than the incidence in placebo-treated patients.

Table 13: Treatment-Emergent Adverse Reactions in an 8-Week Placebo-Controlled Clinical Trial for the Treatment of Bipolar Depression
Body System/Preferred Term | Placebo | SEROQUEL XR
 | (n=140) | (n=137)
Ear And Labyrinth Disorders
Ear Pain | 1% | 2%
Gastrointestinal Disorders
Dry Mouth | 7% | 37%
Constipation | 6% | 8%
Dyspepsia | 1% | 7%
Toothache | 0% | 3%
Abdominal Distension | 0% | 1%
General Disorders and Administration Site Conditions
Fatigue | 2% | 6%
Irritability | 3% | 4%
Immune System Disorders
Seasonal Allergy | 1% | 2%
Infections And Infestations
Viral Gastroenteritis | 1% | 4%
Urinary Tract Infection | 0% | 2%
Sinusitis | 1% | 2%
Investigations
Weight Gain | 1% | 7%
Heart Rate Increased | 0% | 2%
Metabolism and Nutrition Disorder
Increased Appetite | 6% | 12%
Decreased Appetite | 1% | 2%
Musculoskeletal And Connective Tissue Disorders
Arthralgia | 1% | 4%
Back Pain | 1% | 3%
Muscle Spasms | 1% | 3%
Myalgia | 1% | 2%
Neck Pain | 0% | 2%
Nervous System Disorders
Somnolence | 13% | 52%
Extrapyramidal Symptoms | 1% | 4%
Dizziness | 11% | 13%
Paraesthesia | 2% | 3%
Disturbance in Attention | 1% | 2%
Dysarthria | 0% | 2%
Akathisia | 0% | 2%
Hypersomnia | 0% | 2%
Mental Impairment | 0% | 2%
Migraine | 1% | 2%
Restless Legs Syndrome | 1% | 2%
Sinus Headache | 1% | 2%
Psychiatric Disorders
Abnormal Dreams | 0% | 3%
Anxiety | 1% | 2%
Confusional State | 0% | 2%
Disorientation | 0% | 2%
Libido Decreased | 1% | 2%
Renal And Urinary Disorders
Pollakiuria | 1% | 2%
Respiratory, Thoracic And Mediastinal Disorders
Sinus Congestion | 1% | 2%
Skin And Subcutaneous Tissue Disorders
Hyperhidrosis | 1% | 2%
Vascular Disorders
Orthostatic Hypotension | 1% | 2%

In the 6-week placebo-controlled fixed dose adjunctive therapy clinical trials, for MDD, the most commonly observed adverse reactions associated with the use of SEROQUEL XR (incidence of 5% or greater and observed at a rate on SEROQUEL XR and at least twice that of placebo) were somnolence (150 mg: 37%; 300 mg: 43%), dry mouth (150 mg: 27%; 300 mg: 40%), fatigue (150 mg: 14%; 300 mg: 11%), constipation (300 mg only: 11%) and weight increased (300 mg only: 5%).

Table 14 enumerates the incidence, rounded to the nearest percent, of treatment-emergent adverse reactions that occurred during short-term adjunctive therapy of MDD (up to 6 weeks) in 1% or more of patients treated with SEROQUEL XR (at doses of either 150 mg or 300 mg/day) where the incidence in patients treated with SEROQUEL XR was greater than the incidence in placebo-treated patients.

Table 14: Treatment-Emergent Adverse Reaction Incidence in Placebo-Controlled Adjunctive Therapy Clinical Trials for the Treatment of MDD by Fixed Dose
Body System/Preferred Term | Placebo (n=309) | SEROQUEL XR 150 mg (n=315) | SEROQUEL XR 300 mg (n=312)
Ear And Labyrinth Disorders
Vertigo | 1% | 2% | 2%
Eye Disorders
Vision Blurred | 1% | 2% | 1%
Gastrointestinal Disorders
Dry Mouth | 8% | 27% | 40%
Constipation | 4% | 6% | 11%
Nausea | 7% | 7% | 8%
Dyspepsia | 2% | 2% | 3%
Abdominal Distension | 0% | 0% | 1%
Vomiting | 1% | 3% | 1%
General Disorders and Administration Site Conditions
Fatigue | 4% | 14% | 11%
Irritability | 3% | 4% | 2%
Chills | 0% | 1% | 1%
Infections And Infestations
Upper Respiratory Tract Infection | 2% | 3% | 2%
Influenza | 0% | 2% | 1%
Injury, Poisoning And Procedural Complications
Fall | 1% | 2% | 0%
Investigations
Weight Increased | 0% | 3% | 5%
Metabolism And Nutrition Disorders
Increased Appetite | 3% | 3% | 5%
Musculoskeletal And Connective Tissue Disorders
Back pain | 1% | 3% | 3%
Muscle Spasms | 1% | 2% | 1%
Nervous System Disorders
Somnolence | 9% | 37% | 43%
Dizziness | 7% | 11% | 12%
Extrapyramidal Symptoms | 4% | 4% | 6%
Hypersomnia | 0% | 1% | 2%
Dysarthria | 0% | 1% | 1%
Dysgeusia | 0% | 1% | 1%
Lethargy | 1% | 2% | 1%
Akathisia | 1% | 2% | 2%
Psychiatric Disorders
Abnormal Dreams | 1% | 2% | 2%
Anxiety | 1% | 2% | 2%
Restlessness | 1% | 1% | 2%
Libido Decreased | 0% | 0% | 1%
Depression | 1% | 2% | 1%

Adverse Reactions Occurring at an Incidence of 5% or More Among SEROQUEL XR Treated Patients in Long-Term, Placebo-Controlled Trials

In a longer-term placebo-controlled trial, adult patients with schizophrenia who remained clinically stable on SEROQUEL XR during open-label treatment for at least 4 months were randomized to placebo (n=103) or to continue on their current SEROQUEL XR (n=94) for up to 12 months of observation for possible relapse, the adverse reactions reported were generally consistent with those reported in the short-term, placebo-controlled trials. Insomnia (8.5%) and headache (7.4%) were the only adverse events reported by 5% or more patients.

Adverse Reactions that occurred in <5% of patients and were considered drug-related (incidence greater than placebo and consistent with known pharmacology of drug class) in order of decreasing frequency:

heart rate increased, hypotension, weight increased, tremor, akathisia, increased appetite, blurred vision, postural dizziness, pyrexia, dysarthria, dystonia, drooling, syncope, tardive dyskinesia, dysphagia, leukopenia, and rash.

Adverse Reactions in clinical trials with quetiapine and not listed elsewhere in the label:

nightmares, peripheral edema, rhinitis, eosinophilia, hypersensitivity, elevations in gamma-GT levels, and elevations in serum creatine phosphokinase (not associated with NMS).

Extrapyramidal Symptoms (EPS):

Dystonia

Class Effect: Symptoms of dystonia, prolonged abnormal contractions of muscle groups, may occur in susceptible individuals during the first few days of treatment. Dystonic symptoms include: spasm of the neck muscles, sometimes progressing to tightness of the throat, swallowing difficulty, difficulty breathing, and/or protrusion of the tongue. While these symptoms can occur at low doses, they occur more frequently and with greater severity with high potency and at higher doses of first generation antipsychotic drugs. An elevated risk of acute dystonia is observed in males and younger age groups.

Four methods were used to measure EPS: (1) Simpson-Angus total score (mean change from baseline) which evaluates Parkinsonism and akathisia, (2) Barnes Akathisia Rating Scale (BARS) Global Assessment Score, (3) incidence of spontaneous complaints of EPS (akathisia, akinesia, cogwheel rigidity, extrapyramidal syndrome, hypertonia, hypokinesia, neck rigidity, and tremor), and (4) use of anticholinergic medications to treat emergent EPS.

Adults: In placebo-controlled clinical trials with quetiapine, utilizing doses up to 800 mg per day, the incidence of any adverse reactions potentially related to EPS ranged from 8% to 11% for quetiapine and 4% to 11% for placebo.

In three-arm placebo-controlled clinical trials for the treatment of schizophrenia, utilizing doses between 300 mg and 800 mg of SEROQUEL XR, the incidence of any adverse reactions potentially related to EPS was 8% for SEROQUEL XR and 8% for SEROQUEL (without evidence of being dose related), and 5% in the placebo group. In these studies, the incidence of the individual adverse reactions (akathisia, extrapyramidal disorder, tremor, dyskinesia, dystonia, restlessness, and muscle rigidity) was generally low and did not exceed 3% for any treatment group.

At the end of treatment, the mean change from baseline in SAS total score and BARS Global Assessment score was similar across the treatment groups. The use of concomitant anticholinergic medications was infrequent and similar across the treatment groups. The incidence of extrapyramidal symptoms was consistent with that seen with the profile of SEROQUEL in schizophrenia patients.

Table 15: Adverse Experiences Associated with Extrapyramidal Symptoms in Placebo-controlled Clinical Trials for Schizophrenia

Preferred term | Placebo; (N=319) |  | SEROQUEL XR 300 mg/day; (N=91) |  | SEROQUEL XR 400 mg/day; (N=227) |  | SEROQUEL XR 600 mg/day; (N=310) |  | SEROQUEL XR 800 mg/day; (N=323) |  | All Doses; (N=951)
 | n | % | n | % | n | % | n | % | n | % | n | %
Dystonic event | 0 | 0.0 | 3 | 3.3 | 0 | 0.0 | 4 | 1.3 | 1 | 0.3 | 8 | 0.8
Parkinsonism | 4 | 1.3 | 1 | 1.1 | 3 | 1.3 | 11 | 3.6 | 7 | 2.2 | 22 | 2.3
Akathisia | 4 | 1.3 | 0 | 0.0 | 3 | 1.3 | 7 | 2.3 | 7 | 2.2 | 17 | 1.8
Dyskinetic event | 2 | 0.6 | 2 | 2.2 | 1 | 0.4 | 1 | 0.3 | 1 | 0.3 | 5 | 0.5
Other extrapyramidal event | 7 | 2.2 | 3 | 3.3 | 4 | 1.8 | 7 | 2.3 | 12 | 3.7 | 26 | 2.7

In a placebo-controlled clinical trial for the treatment of bipolar mania, utilizing the dose range of 400-800 mg/day of SEROQUEL XR, the incidence of any adverse reactions potentially related to EPS was 6.6% for SEROQUEL XR and 3.8% in the placebo group. In this study, the incidence of the individual adverse reactions (akathisia, extrapyramidal disorder, tremor, dystonia, restlessness, and cogwheel rigidity) did not exceed 2.0% for any adverse reaction.

Table 16: Adverse Experiences Associated with Extrapyramidal Symptoms in a Placebo-controlled Clinical Trial for Bipolar Mania

Preferred term | Placebo; (N=160) |  | SEROQUEL XR; (N=151)
Preferred term | n | % | n | %
Dystonic event | 0 | 0.0 | 1 | 0.7
Parkinsonism | 3 | 1.9 | 4 | 2.7
Akathisia | 1 | 0.6 | 2 | 1.3
Other extrapyramidal event | 2 | 1.3 | 3 | 2.0

In a placebo-controlled clinical trial for the treatment of bipolar depression utilizing 300 mg of SEROQUEL XR, the incidence of any adverse reactions potentially related to EPS was 4.4% for SEROQUEL XR and 0.7% in the placebo group. In this study, the incidence of the individual adverse reactions (akathisia, extrapyramidal disorder, tremor, dystonia, hypertonia) did not exceed 1.5% for any individual adverse reaction.

Table 17: Adverse Experiences Associated with Extrapyramidal Symptoms in a Placebo-controlled Clinical Trial for Bipolar Depression

Preferred term | Placebo; (N=140) |  | SEROQUEL XR; (N=137)
Preferred term | n | % | n | %
Dystonic event | 0 | 0.0 | 2 | 1.5
Parkinsonism | 1 | 0.7 | 1 | 0.7
Akathisia | 0 | 0.0 | 2 | 1.5
Other extrapyramidal event | 0 | 0.0 | 1 | 0.7

In two placebo-controlled short-term adjunctive therapy clinical trials for the treatment of MDD utilizing between 150 mg and 300 mg of SEROQUEL XR, the incidence of any adverse reactions potentially related to EPS was 5.1% for SEROQUEL XR and 4.2% for the placebo group.

Table 18 shows the percentage of patients experiencing adverse reactions potentially associated with EPS in adjunct clinical trials for MDD by dose:

Table 18: Adverse Reactions Potentially Associated with EPS in MDD Trials by Dose, Adjunctive Therapy Clinical Trials (6 weeks duration)

Preferred term | Placebo; (N=309) |  | SEROQUEL XR 150 mg/day; (N=315) |  | SEROQUEL XR 300 mg/day; (N=312) |  | All Doses; (N=627)
Preferred term | n | % | n | % | n | % | n | %
Dystonic event | 0 | 0.0 | 1 | 0.3 | 0 | 0.0 | 1 | 0.2
Parkinsonism | 5 | 1.6 | 3 | 1.0 | 4 | 1.3 | 7 | 1.1
Akathisia | 3 | 1.0 | 5 | 1.6 | 8 | 2.6 | 13 | 2.1
Dyskinetic event | 0 | 0.0 | 0 | 0.0 | 1 | 0.3 | 1 | 0.2
Other extrapyramidal event | 5 | 1.6 | 5 | 1.6 | 7 | 2.2 | 12 | 1.9

Children and Adolescents: Safety and effectiveness of SEROQUEL XR have not been established in pediatric patients and SEROQUEL XR is not approved for patients under the age of 18 years. In a short-term placebo-controlled monotherapy trial in adolescent patients with schizophrenia (6-week duration), the aggregated incidence of extrapyramidal symptoms was 12.9% for SEROQUEL and 5.3% for placebo, though the incidence of the individual adverse events (eg, akathisia, tremor, extrapyramidal disorder, hypokinesia, restlessness, psychomotor hyperactivity, muscle rigidity, dyskinesia) did not exceed 4.1% in any treatment group. In a short-term placebo-controlled monotherapy trial in children and adolescent patients with bipolar mania (3-week duration), the aggregated incidence of extrapyramidal symptoms was 3.6% for SEROQUEL and 1.1% for placebo.

Table 19 below presents a listing of patients with adverse experiences potentially associated with EPS in the short-term placebo-controlled monotherapy trial in adolescent patients with schizophrenia (6-week duration).

Table 19 Adverse experiences potentially associated with EPS in the short-term placebo-controlled monotherapy trial in adolescent patients with schizophrenia (6-week duration).

Preferred term | Placebo; (N=75) |  | SEROQUEL 400 mg/day; (N=73) |  | SEROQUEL 800 mg/day; (N=74) |  | All SEROQUEL; (N=147)
Preferred term | n | :% | n | % | n | % | n | %
Dystonic event | 0 | 0.0 | 2 | 2.7 | 0 | 0.0 | 2 | 1.4
Parkinsonism | 2 | 2.7 | 4 | 5.5 | 4 | 5.4 | 8 | 5.4
Akathisia | 3 | 4.0 | 3 | 4.1 | 4 | 5.4 | 7 | 4.8
Dyskinetic event | 0 | 0.0 | 2 | 2.7 | 0 | 0.0 | 2 | 1.4
Other extrapyramidal event | 0 | 0.0 | 2 | 2.7 | 2 | 2.7 | 4 | 2.7

Table 20 below presents a listing of patients with Adverse Experiences potentially associated with EPS in a short-term placebo-controlled monotherapy trial in children and adolescent patients with bipolar mania (3-week duration)

Table 20: Adverse experiences potentially associated with EPS in a short-term placebo-controlled monotherapy trial in children and adolescent patients with bipolar mania (3-week duration)
Preferred term | Placebo; (N=90) |  | SEROQUEL 400 mg/day; (N=95) |  | SEROQUEL 600 mg/day; (N=98) |  | All SEROQUEL; (N=193)
Preferred term | n | % | n | % | n | % | n | %
Parkinsonism | 1 | 1.1 | 2 | 2.1 | 1 | 1.0 | 3 | 1.6
Akathisia | 0 | 0.0 | 1 | 1.0 | 1 | 1.0 | 2 | 1.0
Other extrapyramidal event | 0 | 0.0 | 1 | 1.1 | 1 | 1.0 | 2 | 1.0

Children and Adolescents: Safety and effectiveness of SEROQUEL XR have not been established in pediatric patients and SEROQUEL XR is not approved for patients under the age of 18 years. In acute placebo-controlled trials in children and adolescent patients with schizophrenia (6-week duration) or bipolar mania (3-week duration), the incidence of increased appetite was 7.6% for SEROQUEL compared to 2.4% for placebo. In a 26-week open-label study that enrolled patients from the above two pediatric trials, the incidence of increased appetite was 7% for SEROQUEL.

6.2 Vital Signs and Laboratory Values

Hyperglycemia, hyperlipidemia, weight gain, orthostatic hypotension and changes in thyroid hormone levels have been reported with quetiapine. Increases in blood pressure have also been reported with quetiapine in children and adolescents [see Warnings and Precautions (5.4, 5.5, 5.6, 5.8, 5.9 and 5.14)].

Laboratory Changes:

Neutrophil Counts

In three-arm SEROQUEL XR placebo-controlled monotherapy clinical trials, among patients with a baseline neutrophil count ≥ 1.5 x 10^9/L, the incidence of at least one occurrence of neutrophil count <1.5 x 10^9/L was 1.5% in patients treated with SEROQUEL XR and 1.5% for SEROQUEL, compared to 0.8% in placebo-treated patients.

In placebo-controlled monotherapy clinical trials involving 3368 patients on quetiapine fumarate and 1515 on placebo, the incidence of at least one occurrence of neutrophil count <1.0 x 10^9/L among patients with a normal baseline neutrophil count and at least one available follow up laboratory measurement was 0.3% (10/2967) in patients treated with quetiapine, compared to 0.1% (2/1349) in patients treated with placebo. Patients with a pre-existing low WBC or a history of drug induced leukopenia/neutropenia should have their complete blood count (CBC) monitored frequently during the first few months of therapy and should discontinue SEROQUEL XR at the first sign of a decline in WBC in absence of other causative factors [see Warnings and Precautions (5.10)].

Decreased Hemoglobin

In short-term placebo-controlled trials, decreases in hemoglobin to ≤ 13 g/dL males, ≤ 12 g/dL females on at least one occasion occurred in 8.3% (594/7155) of quetiapine-treated patients compared to 6.2% (219/3536) of patients treated with placebo. In a database of controlled and uncontrolled clinical trials, decreases in hemoglobin to ≤ 13 g/dL males, ≤ 12 g/dL females on at least one occasion occurred in 11% (2277/20729) of quetiapine-treated patients.

ECG Changes:

2.5% of SEROQUEL XR patients, and 2.3% of placebo patients, had tachycardia (>120 bpm) at any time during the trials. SEROQUEL XR was associated with a mean increase in heart rate, assessed by ECG, of 6.3 beats per minute compared to a mean increase of 0.4 beats per minute for placebo. This is consistent with the rates for SEROQUEL. The incidence of adverse reactions of tachycardia was 1.9% for SEROQUEL XR compared to 0.5% for placebo. SEROQUEL use was associated with a mean increase in heart rate, assessed by ECG, of 7 beats per minute compared to a mean increase of 1 beat per minute among placebo patients. The slight tendency for tachycardia may be related to quetiapine’s potential for inducing orthostatic changes [see Warnings and Precautions (5.8)].

Children and Adolescents: Safety and effectiveness of SEROQUEL XR have not been established in pediatric patients. In the acute (6-week) schizophrenia trial in adolescents, potentially clinically significant increases in heart rate (> 110 bpm) occurred in 5.2% of patients receiving SEROQUEL 400 mg and 8.5% of patients receiving SEROQUEL 800 mg compared to 0% of patients receiving placebo. Mean increases in heart rate were 3.8 bpm and 11.2 bpm for SEROQUEL 400 mg and 800 mg groups, respectively, compared to a decrease of 3.3 bpm in the placebo group [see Warnings and Precautions (5.8)].

In the acute (3-week) bipolar mania trial in children and adolescents, potentially clinically significant increases in heart rate (> 110 bpm) occurred in 1.1% of patients receiving SEROQUEL 400 mg and 2.4% of patients receiving SEROQUEL 600 mg compared to 0% of patients receiving placebo. Mean increases in heart rate were 12.8 bpm and 13.4 bpm for SEROQUEL 400 mg and 600 mg groups, respectively, compared to a decrease of 1.7 bpm in the placebo group [see Warnings and Precautions (5.8)].

6.3 Post Marketing Experience

The following adverse reactions were identified during post approval use of SEROQUEL. Because these reactions are reported voluntarily from a population of uncertain size, it is not always possible to reliably estimate their frequency or establish a causal relationship to drug exposure.

Adverse reactions reported since market introduction which were temporally related to SEROQUEL therapy include anaphylactic reaction and galactorrhea.

Other adverse reactions reported since market introduction, which were temporally related to SEROQUEL therapy, but not necessarily causally related, include the following: agranulocytosis, cardiomyopathy, hyponatremia, myocarditis, rhabdomyolysis, syndrome of inappropriate antidiuretic hormone secretion (SIADH), Stevens-Johnson syndrome (SJS), and decreased platelets.

In post-marketing clinical trials, elevations in total cholesterol (predominantly LDL cholesterol), dyspnea, palpitations, somnambulism (and other related events) and hypothermia have been reported.

7 DRUG INTERACTIONS

The risks of using SEROQUEL XR in combination with other drugs have not been extensively evaluated in systematic studies. Given the primary CNS effects of SEROQUEL XR, caution should be used when it is taken in combination with other centrally acting drugs. Quetiapine potentiated the cognitive and motor effects of alcohol in a clinical trial in subjects with selected psychotic disorders, and alcoholic beverages should be limited while taking quetiapine.

Because of its potential for inducing hypotension, SEROQUEL XR may enhance the effects of certain antihypertensive agents.

SEROQUEL XR may antagonize the effects of levodopa and dopamine agonists.

The use of quetiapine should be avoided in combination with drugs known to increase QT interval, and caution should be exercised when quetiapine is used in combination with drugs known to cause electrolyte imbalance [see Warnings and Precautions (5.12)].

There have been literature reports suggesting false positive results in urine enzyme immunoassays for methadone and tricyclic antidepressants in patients who have taken quetiapine. Caution should be exercised in the interpretation of positive urine drug screen results for these drugs, and confirmation by alternative analytical technique (e.g. chromatographic methods) should be considered.

7.1 The Effect of Other Drugs on Quetiapine

Phenytoin

Coadministration of quetiapine (250 mg three times/day) and phenytoin (100 mg three times/day) increased the mean oral clearance of quetiapine by 5-fold. Increased doses of SEROQUEL XR may be required to maintain control of symptoms of schizophrenia in patients receiving quetiapine and phenytoin, or other hepatic enzyme inducers (eg, carbamazepine, barbiturates, rifampin, glucocorticoids). Caution should be taken if phenytoin is withdrawn and replaced with a non-inducer (eg, valproate) [see Dosage and Administration (2)].

Divalproex

Coadministration of quetiapine (150 mg twice daily) and divalproex (500 mg twice daily) increased the mean maximum plasma concentration of quetiapine at steady-state by 17% without affecting the extent of absorption or mean oral clearance.

Thioridazine

Thioridazine (200 mg twice daily) increased the oral clearance of quetiapine (300 mg twice daily) by 65%.

Cimetidine

Administration of multiple daily doses of cimetidine (400 mg three times daily for 4 days) resulted in a 20% decrease in the mean oral clearance of quetiapine (150 mg three times daily). Dosage adjustment for quetiapine is not required when it is given with cimetidine.

P450 3A Inhibitors

Coadministration of ketoconazole (200 mg once daily for 4 days), a potent inhibitor of cytochrome P450 3A, reduced oral clearance of quetiapine by 84%, resulting in a 335% increase in maximum plasma concentration of quetiapine. Caution (reduced dosage) is indicated when SEROQUEL XR is administered with ketoconazole and other inhibitors of cytochrome P450 3A (eg, itraconazole, fluconazole, erythromycin, protease inhibitors).

Fluoxetine, Imipramine, Haloperidol, and Risperidone

Coadministration of fluoxetine (60 mg once daily), imipramine (75 mg twice daily), haloperidol (7.5 mg twice daily), or risperidone (3 mg twice daily) with quetiapine (300 mg twice daily) did not alter the steady-state pharmacokinetics of quetiapine.

7.2 Effect of Quetiapine on Other Drugs

Lorazepam

The mean oral clearance of lorazepam (2 mg, single dose) was reduced by 20% in the presence of quetiapine administered as 250 mg three times daily dosing.

Divalproex

The mean maximum concentration and extent of absorption of total and free valproic acid at steady-state were decreased by 10 to 12% when divalproex (500 mg twice daily) was administered with quetiapine (150 mg twice daily). The mean oral clearance of total valproic acid (administered as divalproex 500 mg twice daily) was increased by 11% in the presence of quetiapine (150 mg twice daily). The changes were not significant.

Lithium

Concomitant administration of quetiapine (250 mg three times daily) with lithium had no effect on any of the steady-state pharmacokinetic parameters of lithium.

Antipyrine

Administration of multiple daily doses up to 750 mg/day (on a three times daily schedule) of quetiapine to subjects with selected psychotic disorders had no clinically relevant effect on the clearance of antipyrine or urinary recovery of antipyrine metabolites. These results indicate that quetiapine does not significantly induce hepatic enzymes responsible for cytochrome P450 mediated metabolism of antipyrine.

8 USE IN SPECIFIC POPULATIONS

8.1 Pregnancy

Pregnancy Category C:

There are no adequate and well-controlled studies of SEROQUEL XR use in pregnant women. In limited published literature, there were no major malformations associated with quetiapine exposure during pregnancy. In animal studies, embryo-fetal toxicity occurred. Quetiapine should be used during pregnancy only if the potential benefit justifies the potential risk to the fetus.

There are limited published data on the use of quetiapine for treatment of schizophrenia and other psychiatric disorders during pregnancy. In a prospective observational study, 21 women exposed to quetiapine and other psychoactive medications during pregnancy delivered infants with no major malformations. Among 42 other infants born to pregnant women who used quetiapine during pregnancy, there were no major malformations reported (one study of 36 women, 6 case reports). Due to the limited number of exposed pregnancies, these postmarketing data do not reliably estimate the frequency or absence of adverse outcomes.

When pregnant rats and rabbits were exposed to quetiapine during organogenesis, there was no increase in the incidence of major malformations in fetuses at doses up to 2.4 times the maximum recommended human dose for schizophrenia (MRHD, 800 mg/day on a mg/m^2 basis); however, there was evidence of embryo-fetal toxicity. In rats, delays in skeletal ossification occurred at 0.6 and 2.4 times the MRHD and in rabbits at 1.2 and 2.4 times the MRHD. At 2.4 times the MRHD, there was an increased incidence of carpal/tarsal flexure (minor soft tissue anomaly) in rabbit fetuses and decreased fetal weights in both species. Maternal toxicity (decreased body weights and/or death) occurred at 2.4 times the MRHD in rats and at 0.6-2.4 times the MRHD (all doses) in rabbits.

In a peri/postnatal reproductive study in rats, no drug-related effects were observed when pregnant dams were treated with quetiapine at doses 0.01, 0.12, and 0.24 times the MRHD. However, in a preliminary peri/postnatal study, there were increases in fetal and pup death, and decreases in mean litter weight at 3.0 times the MRHD.

Non-Teratogenic Effects

Neonates exposed to antipsychotic drugs (including SEROQUEL XR), during the third trimester of pregnancy are at risk for extrapyramidal and/or withdrawal symptoms following delivery. There have been reports of agitation, hypertonia, hypotonia, tremor, somnolence, respiratory distress and feeding disorder in these neonates. These complications have varied in severity; while in some cases symptoms have been self-limited, in other cases neonates have required intensive care unit support and prolonged hospitalization.

SEROQUEL XR should be used during pregnancy only if the potential benefit justifies the potential risk to the fetus.

8.2 Labor and Delivery

The effect of SEROQUEL XR on labor and delivery in humans is unknown.

8.3 Nursing Mothers

SEROQUEL XR was excreted into human milk. It is recommended that women receiving SEROQUEL XR should not breast feed.

In published case reports, the level of quetiapine in breast milk ranged from undetectable to 170 μg/L. The estimated infant dose ranged from 0.09% to 0.43% of the weight-adjusted maternal dose. Based on a limited number (N=8) of mother/infant pairs, calculated infant daily doses range from less than 0.01 mg/kg (at a maternal daily dose up to 100 mg quetiapine) to 0.1 mg/kg (at a maternal daily dose of 400 mg).

8.4 Pediatric Use

Safety and effectiveness of SEROQUEL XR have not been established in pediatric patients and SEROQUEL XR is not approved for patients under the age of 18 years [see Warnings and Precautions (5) and Adverse Reactions (6)].

In general, the adverse reactions observed in children and adolescents during the clinical trials with SEROQUEL were similar to those in the adult population with few exceptions. Increases in systolic and diastolic blood pressure occurred in children and adolescents and did not occur in adults. Orthostatic hypotension occurred more frequently in adults (4-7%) compared to children and adolescents (< 1%).

8.5 Geriatric Use

Sixty-eight patients in clinical studies with SEROQUEL XR were 65 years of age or over. In general, there was no indication of any different tolerability of SEROQUEL XR in the elderly compared to younger adults. Nevertheless, the presence of factors that might decrease pharmacokinetic clearance, increase the pharmacodynamic response to SEROQUEL XR, or cause poorer tolerance or orthostasis, should lead to consideration of a lower starting dose, slower titration, and careful monitoring during the initial dosing period in the elderly. The mean plasma clearance of quetiapine was reduced by 30% to 50% in elderly patients when compared to younger patients [see Dosage and Administration (2.4) and Pharmacokinetics (12.3)].

8.6 Renal Impairment

Clinical experience with SEROQUEL XR in patients with renal impairment [see Clinical Pharmacology (12.3)] is limited.

8.7 Hepatic Impairment

Since quetiapine is extensively metabolized by the liver, higher plasma levels are expected in the hepatically impaired population, and dosage adjustment may be needed [see Dosage and Administration (2.3) and Clinical Pharmacology (12.3)].

9 DRUG ABUSE AND DEPENDENCE

9.1 Controlled Substance

SEROQUEL XR is not a controlled substance.

9.2 Abuse

SEROQUEL XR has not been systematically studied in animals or humans for its potential for abuse, tolerance or physical dependence. While the clinical trials did not reveal any tendency for any drug-seeking behavior, these observations were not systematic and it is not possible to predict on the basis of this limited experience the extent to which a CNS-active drug will be misused, diverted, and/or abused once marketed. Consequently, patients should be evaluated carefully for a history of drug abuse, and such patients should be observed closely for signs of misuse or abuse of SEROQUEL XR (eg, development of tolerance, increases in dose, drug-seeking behavior).

10 OVERDOSAGE

10.1 Human Experience

In clinical trials, survival has been reported in acute overdoses of up to 30 grams of quetiapine. Most patients who overdosed experienced no adverse events or recovered fully from the reported events. Death has been reported in a clinical trial following an overdose of 13.6 grams of quetiapine alone. In general, reported signs and symptoms were those resulting from an exaggeration of the drug’s known pharmacological effects, ie, drowsiness and sedation, tachycardia and hypotension. Patients with pre-existing severe cardiovascular disease may be at an increased risk of the effects of overdose [see Warnings and Precautions (5.12)]. One case, involving an estimated overdose of 9600 mg, was associated with hypokalemia and first degree heart block. In post-marketing experience, there were cases reported of QT prolongation with overdose. There were also very rare reports of overdose of SEROQUEL alone resulting in death or coma.

10.2 Management of Overdosage

In case of acute overdosage, establish and maintain an airway and ensure adequate oxygenation and ventilation. Gastric lavage (after intubation, if patient is unconscious) and administration of activated charcoal together with a laxative should be considered. The possibility of obtundation, seizure or dystonic reaction of the head and neck following overdose may create a risk of aspiration with induced emesis. Cardiovascular monitoring should commence immediately and should include continuous electrocardiographic monitoring to detect possible arrhythmias. If antiarrhythmic therapy is administered, disopyramide, procainamide and quinidine carry a theoretical hazard of additive QT-prolonging effects when administered in patients with acute overdosage of SEROQUEL XR. Similarly it is reasonable to expect that the α-adrenergic-blocking properties of bretylium might be additive to those of quetiapine, resulting in problematic hypotension.

There is no specific antidote to SEROQUEL XR. Therefore, appropriate supportive measures should be instituted. The possibility of multiple drug involvement should be considered. Hypotension and circulatory collapse should be treated with appropriate measures such as intravenous fluids and/or sympathomimetic agents (epinephrine and dopamine should not be used, since β stimulation may worsen hypotension in the setting of quetiapine-induced α blockade). In cases of severe extrapyramidal symptoms, anticholinergic medication should be administered. Close medical supervision and monitoring should continue until the patient recovers.

11 DESCRIPTION

SEROQUEL XR (quetiapine fumarate) is a psychotropic agent belonging to a chemical class, the dibenzothiazepine derivatives. The chemical designation is 2-[2-(4-dibenzo [b,f ] [1,4] thiazepin-11-yl-1-piperazinyl)ethoxy]-ethanol fumarate (2:1) (salt). It is present in tablets as the fumarate salt. All doses and tablet strengths are expressed as milligrams of base, not as fumarate salt. Its molecular formula is C42H50N6O4S2•C4H4O4 and it has a molecular weight of 883.11 (fumarate salt). The structural formula is:

Quetiapine fumarate is a white to off-white crystalline powder which is moderately soluble in water.

SEROQUEL XR is supplied for oral administration as 50 mg (peach), 150 mg (white), 200 mg (yellow), 300 mg (pale yellow), and 400 mg (white). All tablets are capsule shaped and film coated.

Inactive ingredients for SEROQUEL XR are lactose monohydrate, microcrystalline cellulose, sodium citrate, hypromellose, and magnesium stearate. The film coating for all SEROQUEL XR tablets contain hypromellose, polyethylene glycol 400 and titanium dioxide. In addition, yellow iron oxide (50, 200 and 300 mg tablets) and red iron oxide (50 mg tablets) are included in the film coating of specific strengths.

Each 50 mg tablet contains 58 mg of quetiapine fumarate equivalent to 50 mg quetiapine. Each 150 mg tablet contains 173 mg of quetiapine fumarate equivalent to 150 mg quetiapine. Each 200 mg tablet contains 230 mg of quetiapine fumarate equivalent to 200 mg quetiapine. Each 300 mg tablet contains 345 mg of quetiapine fumarate equivalent to 300 mg quetiapine. Each 400 mg tablet contains 461 mg of quetiapine fumarate equivalent to 400 mg quetiapine.

12 CLINICAL PHARMACOLOGY

12.1 Mechanism of Action

The mechanism of action of SEROQUEL XR, as with other drugs having efficacy in the treatment of schizophrenia, bipolar disorder and major depressive disorder (MDD), is unknown. However, it has been proposed that the efficacy of SEROQUEL XR in schizophrenia is mediated through a combination of dopamine type 2 (D2) and serotonin type 2A (5HT2A) antagonism. The active metabolite, N-desalkyl quetiapine (norquetiapine), has similar activity at D2, but greater activity at 5HT2A receptors, than the parent drug (quetiapine). Quetiapine’s efficacy in bipolar depression and MDD may partly be explained by the high affinity and potent inhibitory effects that norquetiapine exhibits for the norepinephrine transporter.

Antagonism at receptors other than dopamine and serotonin with similar or greater affinities may explain some of the other effects of quetiapine and norquetiapine: antagonism at histamine H1 receptors may explain the somnolence, antagonism at adrenergic α1b receptors may explain the orthostatic hypotension, and antagonism at muscarinic M1 receptors may explain the anticholinergic effects.

12.2 Pharmacodynamics

Quetiapine and norquetiapine have affinity for multiple neurotransmitter receptors including dopamine D1 and D2, serotonin 5HT1A and 5HT2A, histamine H1, muscarinic M1, and adrenergic α1b and α2 receptors. Quetiapine differs from norquetiapine in having no appreciable affinity for muscarinic M1 receptors whereas norquetiapine has high affinity. Quetiapine and norquetiapine lack appreciable affinity for benzodiazepine receptors.

Receptor Affinities (Ki, nM) for Quetiapine and Norquetiapine
Receptor | Quetiapine | Norquetiapine
Dopamine D1 | 428 | 99.8
Dopamine D2 | 626 | 489
Serotonin 5HT1A | 1040 | 191
Serotonin 5HT2A | 38 | 2.9
Norepinephrine transporter | >10000 | 34.8
Histamine H1 | 4.41 | 1.15
Adrenergic α1b | 14.6 | 46.4
Adrenergic α2 | 617 | 1290
Muscarinic M1 | 1086 | 38.3
Benzodiazepine | >10000 | > 10000

12.3 Pharmacokinetics

Following multiple dosing of quetiapine up to a total daily dose of 800 mg, administered in divided doses, the plasma concentration of quetiapine and norquetiapine, the major active metabolite of quetiapine, were proportional to the total daily dose. Accumulation is predictable upon multiple dosing. Steady-state mean Cmax and AUC of norquetiapine are about 21-27% and 46-56%, respectively of that observed for quetiapine. Elimination of quetiapine is mainly via hepatic metabolism. The mean-terminal half-life is approximately 7 hours for quetiapine and approximately 12 hours for norquetiapine within the clinical dose range. Steady-state concentrations are expected to be achieved within two days of dosing. SEROQUEL XR is unlikely to interfere with the metabolism of drugs metabolized by cytochrome P450 enzymes.

Absorption

Quetiapine fumarate reaches peak plasma concentrations approximately 6 hours following administration. SEROQUEL XR dosed once daily at steady-state has comparable bioavailability to an equivalent total daily dose of SEROQUEL administered in divided doses, twice daily. A high-fat meal (approximately 800 to 1000 calories) was found to produce statistically significant increases in the SEROQUEL XR Cmax and AUC of 44% to 52% and 20% to 22%, respectively, for the 50 mg and 300 mg tablets. In comparison, a light meal (approximately 300 calories) had no significant effect on the Cmax or AUC of quetiapine. It is recommended that SEROQUEL XR be taken without food or with a light meal [see Dosage and Administration (2)].

Distribution

Quetiapine is widely distributed throughout the body with an apparent volume of distribution of 10±4 L/kg. It is 83% bound to plasma proteins at therapeutic concentrations. In vitro, quetiapine did not affect the binding of warfarin or diazepam to human serum albumin. In turn, neither warfarin nor diazepam altered the binding of quetiapine.

Metabolism and Elimination

Following a single oral dose of ^14C-quetiapine, less than 1% of the administered dose was excreted as unchanged drug, indicating that quetiapine is highly metabolized. Approximately 73% and 20% of the dose was recovered in the urine and feces, respectively. The average dose fraction of free quetiapine and its major active metabolite is <5% excreted in the urine.

Quetiapine is extensively metabolized by the liver. The major metabolic pathways are sulfoxidation to the sulfoxide metabolite and oxidation to the parent acid metabolite; both metabolites are pharmacologically inactive. In vitro studies using human liver microsomes revealed that the cytochrome P450 3A4 isoenzyme is involved in the metabolism of quetiapine to its major, but inactive, sulfoxide metabolite and in the metabolism of its active metabolite norquetiapine.

Age

Oral clearance of quetiapine was reduced by 40% in elderly patients (> 65 years, n = 9) compared to young patients (n = 12), and dosing adjustment may be necessary [see Dosage and Administration (2.3)].

Gender

There is no gender effect on the pharmacokinetics of quetiapine.

Race

There is no race effect on the pharmacokinetics of quetiapine.

Smoking

Smoking has no effect on the oral clearance of quetiapine.

Renal Insufficiency

Patients with severe renal impairment (CLcr=10-30 mL/min/1.73m^2, n=8) had a 25% lower mean oral clearance than normal subjects (CLcr>80 mL/min/1.73m^2, n=8), but plasma quetiapine concentrations in the subjects with renal insufficiency were within the range of concentrations seen in normal subjects receiving the same dose. Dosage adjustment is therefore not needed in these patients.

Hepatic Insufficiency

Hepatically impaired patients (n=8) had a 30% lower mean oral clearance of quetiapine than normal subjects. In 2 of the 8 hepatically impaired patients, AUC and Cmax were 3 times higher than those observed typically in healthy subjects. Since quetiapine is extensively metabolized by the liver, higher plasma levels are expected in the hepatically impaired population, and dosage adjustment may be needed [see Dosage and Administration (2.4)].

Drug-Drug Interactions

In vitro enzyme inhibition data suggest that quetiapine and 9 of its metabolites would have little inhibitory effect on in vivo metabolism mediated by cytochromes P450 1A2, 2C9, 2C19, 2D6 and 3A4.

Quetiapine oral clearance is increased by the prototype cytochrome P450 3A4 inducer, phenytoin, and decreased by the prototype cytochrome P450 3A4 inhibitor, ketoconazole. Dose adjustment of quetiapine will be necessary if it is coadministered with phenytoin or ketoconazole [see Dosage and Administration (2.4) and Drug Interactions (7.1)].

Quetiapine oral clearance is not inhibited by the non-specific enzyme inhibitor, cimetidine.

Quetiapine at doses of 750 mg/day did not affect the single dose pharmacokinetics of antipyrine, lithium or lorazepam [see Drug Interactions (7.2)].

13 NONCLINICAL TOXICOLOGY

13.1 Carcinogenesis, Mutagenesis, Impairment of Fertility

Carcinogenesis

Carcinogenicity studies were conducted in C57BL mice and Wistar rats. Quetiapine was administered in the diet to mice at doses of 20, 75, 250, and 750 mg/kg and to rats by gavage at doses of 25, 75, and 250 mg/kg for two years. These doses are equivalent to 0.1, 0.5, 1.5, and 4.5 times the maximum human dose for schizophrenia and bipolar mania (800 mg/day) on a mg/m^2 basis (mice) or 0.3, 0.9, and 3.0 times the maximum human dose on a mg/m^2 basis (rats). There were statistically significant increases in thyroid gland follicular adenomas in male mice at doses of 250 and 750 mg/kg or 1.5 and 4.5 times the maximum human dose on a mg/m^2 basis and in male rats at a dose of 250 mg/kg or 3.0 times the maximum human dose on a mg/m^2 basis. Mammary gland adenocarcinomas were statistically significantly increased in female rats at all doses tested (25, 75, and 250 mg/kg or 0.3, 0.9, and 3.0 times the maximum recommended human dose on a mg/m^2 basis).

Thyroid follicular cell adenomas may have resulted from chronic stimulation of the thyroid gland by thyroid stimulating hormone (TSH) resulting from enhanced metabolism and clearance of thyroxine by rodent liver. Changes in TSH, thyroxine, and thyroxine clearance consistent with this mechanism were observed in subchronic toxicity studies in rat and mouse and in a 1-year toxicity study in rat; however, the results of these studies were not definitive. The relevance of the increases in thyroid follicular cell adenomas to human risk, through whatever mechanism, is unknown.

Antipsychotic drugs have been shown to chronically elevate prolactin levels in rodents. Serum measurements in a 1-year toxicity study showed that quetiapine increased median serum prolactin levels a maximum of 32- and 13-fold in male and female rats, respectively. Increases in mammary neoplasms have been found in rodents after chronic administration of other antipsychotic drugs and are considered to be prolactin-mediated. The relevance of this increased incidence of prolactin-mediated mammary gland tumors in rats to human risk is unknown [see Warnings and Precautions (5.15)].

Mutagenesis

The mutagenic potential of quetiapine was tested in six in vitro bacterial gene mutation assays and in an in vitro mammalian gene mutation assay in Chinese Hamster Ovary cells. However, sufficiently high concentrations of quetiapine may not have been used for all tester strains. Quetiapine did produce a reproducible increase in mutations in one Salmonella typhimurium tester strain in the presence of metabolic activation. No evidence of clastogenic potential was obtained in an in vitro chromosomal aberration assay in cultured human lymphocytes or in the in vivo micronucleus assay in rats.

Impairment of Fertility

Quetiapine decreased mating and fertility in male Sprague-Dawley rats at oral doses of 50 and 150 mg/kg or 0.6 and 1.8 times the maximum human dose on a mg/m^2 basis. Drug-related effects included increases in interval to mate and in the number of matings required for successful impregnation. These effects continued to be observed at 150 mg/kg even after a two-week period without treatment. The no-effect dose for impaired mating and fertility in male rats was 25 mg/kg, or 0.3 times the maximum human dose on a mg/m^2 basis. Quetiapine adversely affected mating and fertility in female Sprague-Dawley rats at an oral dose of 50 mg/kg, or 0.6 times the maximum human dose on a mg/m^2 basis. Drug-related effects included decreases in matings and in matings resulting in pregnancy, and an increase in the interval to mate. An increase in irregular estrus cycles was observed at doses of 10 and 50 mg/kg, or 0.1 and 0.6 times the maximum human dose on a mg/m^2 basis. The no-effect dose in female rats was 1 mg/kg, or 0.01 times the maximum human dose on a mg/m^2 basis.

13.2 Animal Toxicology and/or Pharmacology

Quetiapine caused a dose-related increase in pigment deposition in thyroid gland in rat toxicity studies which were 4 weeks in duration or longer and in a mouse 2-year carcinogenicity study. Doses were 10-250 mg/kg in rats, 75-750 mg/kg in mice; these doses are 0.1-3.0, and 0.1-4.5 times the maximum recommended human dose (on a mg/m^2 basis), respectively. Pigment deposition was shown to be irreversible in rats. The identity of the pigment could not be determined, but was found to be co-localized with quetiapine in thyroid gland follicular epithelial cells. The functional effects and the relevance of this finding to human risk are unknown.

In dogs receiving quetiapine for 6 or 12 months, but not for 1 month, focal triangular cataracts occurred at the junction of posterior sutures in the outer cortex of the lens at a dose of 100 mg/kg, or 4 times the maximum recommended human dose on a mg/m^2 basis. This finding may be due to inhibition of cholesterol biosynthesis by quetiapine. Quetiapine caused a dose-related reduction in plasma cholesterol levels in repeat-dose dog and monkey studies; however, there was no correlation between plasma cholesterol and the presence of cataracts in individual dogs. The appearance of delta 8 cholestanol in plasma is consistent with inhibition of a late stage in cholesterol biosynthesis in these species. There also was a 25% reduction in cholesterol content of the outer cortex of the lens observed in a special study in quetiapine treated female dogs. Drug-related cataracts have not been seen in any other species; however, in a 1-year study in monkeys, a striated appearance of the anterior lens surface was detected in 2/7 females at a dose of 225 mg/kg or 5.5 times the maximum recommended human dose on a mg/m^2 basis.

14 CLINICAL STUDIES

14.1 Schizophrenia

The efficacy of SEROQUEL XR in the treatment of schizophrenia was demonstrated in 1 short-term, 6-week, fixed-dose, placebo-controlled trial of inpatients and outpatients with schizophrenia (n=573) who met DSM IV criteria for schizophrenia. SEROQUEL XR (once daily) was administered as 300 mg on Day 1, and the dose was increased to either 400 mg or 600 mg by Day 2, or 800 mg by Day 3. The primary endpoint was the change from baseline of the Positive and Negative Syndrome Scale (PANSS) total score at the end of treatment (Day 42). SEROQUEL XR doses of 400 mg, 600 mg and 800 mg once daily were superior to placebo in the PANSS total score at Day 42.

In a longer-term trial, clinically stable adult outpatients (n=171) meeting DSM-IV criteria for schizophrenia who remained stable following 16 weeks of open-label treatment with flexible doses of SEROQUEL XR (400 mg/day-800 mg/day) were randomized to placebo or to continue on their current SEROQUEL XR (400 mg/day-800 mg/day) for observation for possible relapse during the double-blind continuation (maintenance) phase. Stabilization during the open-label phase was defined as receiving a stable dose of SEROQUEL XR and having a CGI-S≤4 and a PANSS score ≤60 from beginning to end of this open-label phase (with no increase of ≥10 points in PANSS total score). Relapse during the double-blind phase was defined in terms of a ≥30% increase in the PANSS Total score, or CGI-Improvement score of ≥6, or hospitalization due to worsening of schizophrenia, or need for any other antipsychotic medication. Patients on SEROQUEL XR experienced a statistically significant longer time to relapse than did patients on placebo.

14.2 Bipolar Disorder

Bipolar Mania

The efficacy of SEROQUEL XR in the acute treatment of manic episodes was established in one 3-week, placebo-controlled trial in patients who met DSM-IV criteria for bipolar I disorder with manic or mixed episodes with or without psychotic features (N=316). Patients were hospitalized for a minimum of 4 days at randomization. Patients randomized to SEROQUEL XR received 300 mg on Day 1 and 600 mg on Day 2. Afterwards, the dose could be adjusted between 400 mg and 800 mg per day.

The primary rating instrument used for assessing manic symptoms in these trials was the Young Mania Rating Scale (YMRS), an 11-item clinician-rated scale traditionally used to assess the degree of manic symptoms in a range from 0 (no manic features) to 60 (maximum score). SEROQUEL XR was superior to placebo in the reduction of the YMRS total score at week 3.

The efficacy of SEROQUEL in the treatment of acute manic episodes was also established in 3 placebo-controlled trials in patients who met DSM-IV criteria for bipolar I disorder with manic episodes. These trials included patients with or without psychotic features and excluded patients with rapid cycling and mixed episodes. Of these trials, 2 were monotherapy (12 weeks) and 1 was adjunct therapy (3 weeks) to either lithium or divalproex. Key outcomes in these trials were change from baseline in the YMRS score at 3 and 12 weeks for monotherapy and at 3 weeks for adjunct therapy. Adjunct therapy is defined as the simultaneous initiation or subsequent administration of SEROQUEL with lithium or divalproex.

The results of the trials follow:

Monotherapy

In two 12-week trials (n=300, n=299) comparing SEROQUEL to placebo, SEROQUEL was superior to placebo in the reduction of the YMRS total score at weeks 3 and 12. The majority of patients in these trials taking SEROQUEL were dosed in a range between 400 mg/day and 800 mg/day.

Adjunct Therapy

In a 3-week placebo-controlled trial, 170 patients with bipolar mania (YMRS ≥ 20) were randomized to receive SEROQUEL or placebo as adjunct treatment to lithium or divalproex. Patients may or may not have received an adequate treatment course of lithium or divalproex prior to randomization. SEROQUEL was superior to placebo when added to lithium or divalproex alone in the reduction of YMRS total score. The majority of patients in this trial taking SEROQUEL were dosed in a range between 400 mg/day and 800 mg/day.

Depressive Episodes Associated with Bipolar Disorder

The efficacy of SEROQUEL XR for the acute treatment of depressive episodes associated with bipolar disorder in patients who met DSM-IV criteria for bipolar disorder was established in one 8-week, randomized, double-blind, placebo-controlled study (N=280 outpatients). This study included patients with bipolar I and II disorder, and those with and without a rapid cycling course. Patients randomized to SEROQUEL XR were administered 50 mg on Day 1, 100 mg on Day 2, 200 mg on Day 3, and 300 mg on Day 4 and after.

The primary rating instrument used to assess depressive symptoms was the Montgomery-Asberg Depression Rating Scale (MADRS), a 10-item clinician-rated scale with scores ranging from 0 (no depressive features) to 60 (maximum score). The primary endpoint was the change from baseline in MADRS score at week 8. SEROQUEL XR was superior to placebo in reduction of MADRS score at week 8.

The efficacy of SEROQUEL for the treatment of depressive episodes associated with bipolar disorder was established in 2 identical 8-week, randomized, double-blind, placebo-controlled studies (N=1045). These studies included patients with either bipolar I or II disorder and those with or without a rapid cycling course. Patients randomized to SEROQUEL were administered fixed doses of either 300 mg or 600 mg once daily.

The primary rating instrument used to assess depressive symptoms in these studies was the MADRS. The primary endpoint in both studies was the change from baseline in MADRS score at week 8. In both studies, SEROQUEL was superior to placebo in reduction of MADRS score at week 8. In these studies, no additional benefit was seen with the 600 mg dose. For the 300 mg dose group, statistically significant improvements over placebo were seen in overall quality of life and satisfaction related to various areas of functioning, as measured using the Q-LES-Q(SF).

Maintenance Treatment as an Adjunct to Lithium or Divalproex

The efficacy of SEROQUEL in the maintenance treatment of bipolar I disorder was established in 2 placebo-controlled trials in patients (n=1326) who met DSM-IV criteria for bipolar I disorder. The trials included patients whose most recent episode was manic, depressed, or mixed, with or without psychotic features. In the open-label phase, patients were required to be stable on SEROQUEL plus lithium or divalproex for at least 12 weeks in order to be randomized. On average, patients were stabilized for 15 weeks. In the randomization phase, patients continued treatment with lithium or divalproex and were randomized to receive either SEROQUEL (administered twice daily totaling 400 mg/day to 800 mg/day or placebo). Approximately 50% of the patients had discontinued from the SEROQUEL group by day 280 and 50% of the placebo group had discontinued by day 117 of double-blind treatment. The primary endpoint in these studies was time to recurrence of a mood event (manic, mixed or depressed episode). A mood event was defined as medication initiation or hospitalization for a mood episode; YMRS score ≥ 20 or MADRS score ≥ 20 at 2 consecutive assessments; or study discontinuation due to a mood event.

In both studies, SEROQUEL was superior to placebo in increasing the time to recurrence of any mood event. The treatment effect was present for increasing time to recurrence of both manic and depressed episodes. The effect of SEROQUEL was independent of any specific subgroup (assigned mood stabilizer, sex, age, race, most recent bipolar episode, or rapid cycling course).

14.3 Major Depressive Disorder, Adjunctive Therapy to Antidepressants

The efficacy of SEROQUEL XR as adjunctive therapy to antidepressants in the treatment of MDD was demonstrated in two 6-week placebo-controlled, fixed-dose trials (n=936). SEROQUEL XR 150 mg/day or 300 mg/day was given as adjunctive therapy to existing antidepressant therapy in patients who had previously shown an inadequate response to at least one antidepressant. SEROQUEL XR was administered as 50 mg/day on Days 1 and 2, and increased to 150 mg/day on Day 3 for both dose groups. On Day 5, the dose was increased to 300 mg/day in the 300 mg/day fixed-dose group. Inadequate response was defined as having continued depressive symptoms for the current episode (HAM-D total score of ≥ 20) despite using an antidepressant for 6 weeks at or above the minimally effective labelled dose. The mean HAM-D total score at entry was 24, and 17% of patients scored 28 or greater. Patients were on various antidepressants prior to study entry including SSRI’s (paroxetine, fluoxetine, sertraline, escitalopram, or citalopram), SNRI’s, (duloxetine and venlafaxine,) TCA (amitriptyline) and other (bupropion).

The primary endpoint in these trials was change from baseline to week 6 in the Montgomery-Asberg Depression Rating Scale (MADRS), a 10-item clinician-rated scale used to assess the degree of depressive symptomatology (apparent sadness, reported sadness, inner tension, reduced sleep, reduced appetite, concentration difficulties, lassitude, inability to feel, pessimistic thoughts, and suicidal thoughts) with total scores ranging from 0 (no depressive features) to 60 (maximum score).

SEROQUEL XR 300 mg once daily as adjunctive treatment to other antidepressant therapy was superior to antidepressant alone in reduction of MADRS total score in both trials. SEROQUEL XR 150 mg once daily as adjunctive treatment was superior to antidepressant therapy alone in reduction of MADRS total score in one trial.

16 HOW SUPPLIED/STORAGE AND HANDLING

- 50 mg Tablets peach, film coated, capsule-shaped, biconvex, intagliated tablet with “XR 50” on one side and plain on the other are supplied in
  Bottles of 30 | NDC 54868-6317-0

Store SEROQUEL XR at 25ºC (77ºF); excursions permitted to 15-30ºC (59-86ºF) [See USP].

17 PATIENT COUNSELING INFORMATION

17.1 Information for Patients

[see Medication Guide]

Prescribers or other health professionals should inform patients, their families, and their caregivers about the benefits and risks associated with treatment with SEROQUEL XR and should counsel them in its appropriate use. A patient Medication Guide about “Antidepressant Medicines, Depression and other Serious Mental Illness, and Suicidal Thoughts or Actions” is available for SEROQUEL XR. The prescriber or health professional should instruct patients, their families, and their caregivers to read the Medication Guide and should assist them in understanding its contents. Patients should be given the opportunity to discuss the contents of the Medication Guide and to obtain answers to any questions they may have. The complete text of the Medication Guide is reprinted at the end of this document.

Patients should be advised of the following issues and asked to alert their prescriber if these occur while taking SEROQUEL XR.

Increased Mortality in Elderly Patients with Dementia-Related Psychosis

Patients and caregivers should be advised that elderly patients with dementia-related psychoses treated with atypical antipsychotic drugs are at increased risk of death compared with placebo. Quetiapine is not approved for elderly patients with dementia-related psychosis [see Warnings and Precautions (5.1)].

Clinical Worsening and Suicide Risk

Patients, their families, and their caregivers should be encouraged to be alert to the emergence of anxiety, agitation, panic attacks, insomnia, irritability, hostility, aggressiveness, impulsivity, akathisia (psychomotor restlessness), hypomania, mania, other unusual changes in behavior, worsening of depression, and suicidal ideation, especially early during antidepressant treatment and when the dose is adjusted up or down. Families and caregivers of patients should be advised to look for the emergence of such symptoms on a day-to-day basis, since changes may be abrupt. Such symptoms should be reported to the patient's prescriber or health professional, especially if they are severe, abrupt in onset, or were not part of the patient's presenting symptoms. Symptoms such as these may be associated with an increased risk for suicidal thinking and behavior and indicate a need for very close monitoring and possibly changes in the medication [see Warnings and Precautions (5.2)].

Neuroleptic Malignant Syndrome (NMS)

Patients should be advised to report to their physician any signs or symptoms that may be related to NMS. These may include muscle stiffness and high fever [see Warnings and Precautions (5.3)].

Hyperglycemia and Diabetes Mellitus

Patients should be aware of the symptoms of hyperglycemia (high blood sugar) and diabetes mellitus. Patients who are diagnosed with diabetes, those with risk factors for diabetes, or those that develop these symptoms during treatment should have their blood glucose monitored at the beginning of and periodically during treatment [see Warnings and Precautions (5.4)].

Hyperlipidemia

Patients should be advised that elevations in total cholesterol, LDL-cholesterol and triglycerides and decreases in HDL-cholesterol may occur. Patients should have their lipid profile monitored at the beginning of and periodically during treatment [see Warnings and Precautions (5.5)].

Weight Gain

Patients should be advised that they may experience weight gain. Patients should have their weight monitored regularly [see Warnings and Precautions (5.6)].

Orthostatic Hypotension

Patients should be advised of the risk of orthostatic hypotension (symptoms include feeling dizzy or lightheaded upon standing, which may lead to falls) especially during the period of initial dose titration, and also at times of re-initiating treatment or increases in dose [see Warnings and Precautions (5.8)].

Increased Blood Pressure in Children and Adolescents

Blood pressure should be measured at the beginning of, and periodically during, treatment [see Warnings and Precautions (5.9)].

Leukopenia/Neutropenia

Patients with a pre-existing low WBC or a history of drug induced leukopenia/neutropenia should be advised that they should have their CBC monitored while taking SEROQUEL XR [see Warnings and Precautions (5.10)].

Interference with Cognitive and Motor Performance

Patients should be advised of the risk of somnolence or sedation (which may lead to falls), especially during the period of initial dose titration. Patients should be cautioned about performing any activity requiring mental alertness, such as operating a motor vehicle (including automobiles) or operating machinery, until they are reasonably certain quetiapine therapy does not affect them adversely. Patients should limit consumption of alcohol during treatment with quetiapine [see Warnings and Precautions (5.17)].

Heat Exposure and Dehydration

Patients should be advised regarding appropriate care in avoiding overheating and dehydration [see Warnings and Precautions (5.19)].

Concomitant Medication

As with other medications, patients should be advised to notify their physicians if they are taking, or plan to take, any prescription or over-the-counter drugs [see Warnings and Precautions (5.22)].

Pregnancy and Nursing

Patients should be advised to notify their physician if they become pregnant or intend to become pregnant during therapy. Patients should be advised not to breast feed if they are taking quetiapine [see Use in Specific Populations (8.1 and 8.3)].

17.2 MEDICATION GUIDE

MEDICATION GUIDE

SEROQUEL XR (SER-oh-kwell)

(quetiapine fumarate)

Extended-Release Tablets

Read this Medication Guide before you start taking SEROQUEL XR and each time you get a refill. There may be new information. This Medication Guide does not take the place of talking to your healthcare provider about your medical condition or treatment.

What is the most important information I should know about SEROQUEL XR?

SEROQUEL XR may cause serious side effects, including:

1. Risk of death in the elderly with dementia
2. Risk of suicidal thoughts or actions
3. High blood sugar (hyperglycemia)
4. High fat levels in your blood (increased cholesterol and triglycerides)
5. Weight gain

These serious side effects are described below:

1. Risk of death in the elderly with dementia: Medicines like SEROQUEL XR can increase the risk of death in elderly people who have memory loss (dementia). SEROQUEL XR is not approved for treating psychosis in the elderly with dementia.
2. Risk of suicidal thoughts or actions (antidepressant medicines, depression and other serious mental illnesses, and suicidal thoughts or actions):
  Talk to your, or your family member’s, healthcare provider about:
  - all risks and benefits of treatment with antidepressant medicines.
  - all treatment choices for depression or other serious mental illness.

- Antidepressant medicines may increase suicidal thoughts or actions in some children, teenagers, and young adults within the first few months of treatment.
- Depression and other serious mental illnesses are the most important causes of suicidal thoughts and actions. Some people may have a particularly high risk of having suicidal thoughts or actions. These include people who have (or have a family history of) depression, bipolar illness (also called manic-depressive illness), or suicidal thoughts or actions.
- How can I watch for and try to prevent suicidal thoughts and actions in myself or a family member?
  - Pay close attention to any changes, especially sudden changes, in mood, behaviors, thoughts, or feelings. This is very important when an antidepressant medicine is started or when the dose is changed.
  - Call the healthcare provider right away to report new or sudden changes in mood, behavior, thoughts, or feelings.
  - Keep all follow-up visits with the healthcare provider as scheduled. Call the healthcare provider between visits as needed, especially if you have concerns about symptoms.

Call a healthcare provider right away if you or your family member has any of the following symptoms, especially if they are new, worse, or worry you:

- thoughts about suicide or dying
- attempts to commit suicide
- new or worse depression
- new or worse anxiety
- feeling very agitated or restless
- panic attacks
- trouble sleeping (insomnia)
- new or worse irritability
- acting aggressive, being angry, or violent
- acting on dangerous impulses
- an extreme increase in activity and talking (mania)
- other unusual changes in behavior or mood

What else do I need to know about antidepressant medicines?

- Never stop an antidepressant medicine without first talking to your healthcare provider. Stopping an antidepressant medicine suddenly can cause other symptoms.
- Antidepressants are medicines used to treat depression and other illnesses. It is important to discuss all the risks of treating depression and also the risks of not treating it. Patients and their families or other caregivers should discuss all treatment choices with the healthcare provider, not just the use of antidepressants.
- Antidepressant medicines have other side effects. Talk to the healthcare provider about the side effects of the medicine prescribed for you or your family member.
- Antidepressant medicines can interact with other medicines. Know all of the medicines that you or your family member take. Keep a list of all medicines to show the healthcare provider. Do not start new medicines without first checking with your healthcare provider.
- Not all antidepressant medicines prescribed for children are FDA approved for use in children. Talk to your child’s healthcare provider for more information.

3.High blood sugar (hyperglycemia): High blood sugar can happen if you have diabetes already or if you have never had diabetes. High blood sugar could lead to:

1. Build up of acid in your blood due to ketones (ketoacidosis)
2. Coma
3. Death

Increases in blood sugar can happen in some people who take SEROQUEL XR. Extremely high blood sugar can lead to coma or death. If you have diabetes or risk factors for diabetes (such as being overweight or a family history of diabetes) your healthcare provider should check your blood sugar before you start SEROQUEL XR and during therapy.

Call your doctor if you have any of these symptoms of high blood sugar (hyperglycemia) while taking SEROQUEL XR:

- feel very thirsty
- need to urinate more than usual
- feel very hungry
- feel weak or tired
- feel sick to your stomach
- feel confused, or your breath smells fruity.

4. High fat levels in your blood (increased cholesterol and triglycerides): High fat levels may happen in people treated with SEROQUEL XR. You may not have any symptoms, so your doctor may decide to check your cholesterol and triglycerides during your treatment with SEROQUEL XR.

5. Increase in weight (weight gain): Weight gain is common in people who take SEROQUEL XR so you and your doctor should check your weight regularly. Talk to your doctor about ways to control weight gain, such as eating a healthy, balanced diet, and exercising.

What is SEROQUEL XR?

- SEROQUEL XR is a prescription medicine used to treat schizophrenia in adults.
- SEROQUEL XR is a prescription medicine used to treat bipolar disorder in adults, including:
  - manic episodes associated with bipolar disorder alone or with lithium or divalproex
  - depressive episodes associated with bipolar disorder
  - long-term treatment of bipolar I disorder with lithium or divalproex
- SEROQUEL XR is a prescription medicine used to treat major depressive disorder as add-on treatment with antidepressant medicines when your doctor determines that one antidepressant alone is not enough to treat your depression.

SEROQUEL XR is not approved for patients under 18 years of age.

What should I tell my healthcare provider before taking SEROQUEL XR?

Before taking SEROQUEL XR, tell your healthcare provider if you have or have had:

- diabetes or high blood sugar in you or your family: your healthcare provider should check your blood sugar before you start SEROQUEL XR and also during therapy
- high levels of total cholesterol, triglycerides or LDL-cholesterol or low levels of HDL- cholesterol
- low or high blood pressure
- low white blood cell count
- cataracts
- seizures
- abnormal thyroid tests
- high prolactin levels
- heart problems
- liver problems
- any other medical condition
- pregnancy or plans to become pregnant. It is not known if SEROQUEL XR will harm your unborn baby
- breast-feeding or plans to breast-feed. SEROQUEL XR can pass into your breast milk. You and your healthcare provider should decide if you will take SEROQUEL XR or breast-feed. You should not do both.

Tell the healthcare provider about all the medicines that you take or recently have taken including prescription medicines, nonprescription medicines, herbal supplements and vitamins.

SEROQUEL XR and other medicines may affect each other causing serious side effects. SEROQUEL XR may affect the way other medicines work, and other medicines may affect how SEROQUEL XR works.

Especially tell your healthcare provider if you take or plan to take medicines for:

- depression
- high blood pressure
- Parkinson's disease
- trouble sleeping
- abnormal heart beats or rhythm

Also tell your healthcare provider if you take or plan to take any of these medicines:

- phenytoin, divalproex or carbamazepine (for epilepsy)
- barbiturates (to help you sleep)
- rifampin (for tuberculosis)
- glucocorticoids (steroids for inflammation)
- thioridazine (an antipsychotic)
- ketoconazole, fluconazole or itraconazole (for fungal infections)
- erythromycin (an antibiotic)
- protease inhibitors (for HIV)

This is not a complete list of medicines that can affect or be affected by SEROQUEL XR. Your doctor can tell you if it is safe to take SEROQUEL XR with your other medicines. Do not start or stop any medicines while taking SEROQUEL XR without talking to your healthcare provider first. Know the medicines you take. Keep a list of your medicines to show your healthcare provider and pharmacist when you get a new medicine.

Tell your healthcare provider if you are having a urine drug screen because SEROQUEL XR may affect your test results. Tell those giving the test that you are taking SEROQUEL XR.

How should I take SEROQUEL XR?

- Take SEROQUEL XR exactly as your healthcare provider tells you to take it. Do not change the dose yourself.
- Take SEROQUEL XR by mouth, with a light meal or without food.
- SEROQUEL XR should be swallowed whole and not split, chewed or crushed.
- If you feel you need to stop SEROQUEL XR, talk with your healthcare provider first.

If you suddenly stop taking SEROQUEL XR, you may experience side effects such as trouble sleeping or trouble staying asleep (insomnia), nausea, and vomiting.

- If you miss a dose, take it as soon as you remember. If it is close to the next dose, skip the missed dose. Just take the next dose at your regular time. Do not take 2 doses at the same time unless your healthcare provider tells you to. If you are not sure about your dosing, call your healthcare provider.
- If you take too much SEROQUEL XR, call your healthcare provider or poison control center at 1-800-222-1222 right away or go to the nearest hospital emergency room.

What should I avoid while taking SEROQUEL XR?

Do not drive, operate machinery, or do other dangerous activities until you know how SEROQUEL XR affects you. SEROQUEL XR may make you drowsy.

- Avoid getting overheated or dehydrated.
  - Do not over-exercise.
  - In hot weather, stay inside in a cool place if possible.
  - Stay out of the sun. Do not wear too much or heavy clothing.
  - Drink plenty of water.
- Do not drink alcohol while taking SEROQUEL XR. It may make some side effects of SEROQUEL XR worse.

What are possible side effects of SEROQUEL XR?

Serious side effects have been reported with SEROQUEL XR including:

Also see “What is the most important information I should know about SEROQUEL XR?” at the beginning of this Medication Guide.

- Neuroleptic malignant syndrome (NMS): NMS is a rare but very serious condition that can happen in people who take antipsychotic medicines, including SEROQUEL XR. NMS can cause death and must be treated in a hospital. Call your doctor right away if you become severely ill and have some or all of these symptoms:
- high fever
- excessive sweating
- rigid muscles
- confusion
- changes in your breathing, heartbeat, and blood pressure
- Tardive dyskinesia: Tell your healthcare provider about any movements you cannot control in your face, tongue, or other body parts. These may be signs of a serious condition. Tardive dyskinesia may not go away, even if you stop taking SEROQUEL XR. Tardive dyskinesia may also start after you stop taking SEROQUEL XR.
- Orthostatic hypotension (decreased blood pressure): lightheadedness or fainting caused by a sudden change in heart rate and blood pressure when rising too quickly from a sitting or lying position.
- Increases in blood pressure: reported in children and teenagers. Your healthcare provider should check blood pressure in children and adolescents before starting SEROQUEL XR and during therapy. SEROQUEL XR is not approved for patients under 18 years of age.
- Low white blood cell count
- Cataracts
- Seizures
- Abnormal thyroid tests: Your healthcare provider may do blood tests to check your thyroid hormone level.
- Increases in prolactin levels: Your healthcare provider may do blood tests to check your prolactin levels.
- Increases in liver enzymes: Your healthcare provider may do blood tests to check your liver enzyme levels.
- Long lasting and painful erection
- Difficulty swallowing

Common possible side effects with SEROQUEL XR include:

- drowsiness
- dry mouth
- constipation
- dizziness
- increased appetite
- upset stomach
- weight gain
- fatigue
- disturbance in speech and language
- stuffy nose

These are not all the possible side effects of SEROQUEL XR. For more information, ask your healthcare provider or pharmacist.

Call your healthcare provider for medical advice about side effects. You may report side effects to FDA at 1-800-FDA-1088.

How should I store SEROQUEL XR?

- Store SEROQUEL XR at room temperature, between 59°F to 86°F (15°C to 30°C).
- Keep SEROQUEL XR and all medicines out of the reach of children.

General information about SEROQUEL XR

Do not take SEROQUEL XR unless your healthcare provider has prescribed it for you for your condition. Do not share SEROQUEL XR with other people, even if they have the same condition. It may harm them.

This Medication Guide provides a summary of important information about SEROQUEL XR. For more information about SEROQUEL XR, talk with your healthcare provider or pharmacist or call 1-800-236-9933. You can ask your healthcare provider for information about SEROQUEL XR that is written for health professionals.

What are the ingredients in SEROQUEL XR?

Active ingredient: quetiapine fumarate

Inactive ingredients: lactose monohydrate, microcrystalline cellulose, sodium citrate, hypromellose, and magnesium stearate. The film coating for all SEROQUEL XR tablets contain hypromellose, polyethylene glycol 400 and titanium dioxide. In addition, yellow iron oxide (50, 200 and 300 mg tablets) and red iron oxide (50 mg tablets) are included in the film coating of specific strengths.

The symptoms of Schizophrenia include:

- Having lost touch with reality (psychosis)
- Seeing things that are not there or hearing voices (hallucinations)
- Believing things that are not true (delusions)
- Being suspicious (paranoia).

The symptoms of Bipolar Disorder include:

- General symptoms of bipolar disorder include extreme mood swings, along with other specific symptoms and behaviors. These mood swings, or "episodes," include manic (highs) and depressive (lows)
- Common symptoms of a manic episode include feeling extremely happy, being very irritable, restless, talking too fast and too much, and having more energy and needing less sleep than usual
- Common symptoms of a depressive episode include feelings of sadness or emptiness, increased tearfulness, a loss of interest in activities you once enjoyed, loss of energy, difficulty concentrating or making decisions, feelings of worthlessness or guilt, changes in sleep or appetite.
- Thoughts of death or suicide.

The symptoms of Major Depressive Disorder (MDD) include:

- Feeling of sadness, emptiness and increased tearfulness
- Loss of interest in activities that you once enjoyed and loss of energy
- Problems focusing and making decisions
- Feeling of worthlessness or guilt
- Changes in sleep or eating patterns
- Thoughts of death or suicide
- MDD symptoms last most of the day, nearly every day for at least two weeks, and interfere with daily life at home and at work.

This Medication Guide has been approved by the U.S. Food and Drug Administration.

SEROQUEL XR is a trademark of the AstraZeneca group of companies.

©AstraZeneca 2011

Distributed by:

AstraZeneca Pharmaceuticals LP

Wilmington, DE 19850

SIC 35537–XX

Rev. 11/2011

Relabeling and Repackaging by:
Physicians Total Care, Inc.
Tulsa, Oklahoma 74146

PACKAGE LABEL PRINCIPAL DISPLAY PANEL

SEROQUEL XR (SER-oh-kwell)
(quetiapine fumarate)
Extended-Release Tablets
50 mg